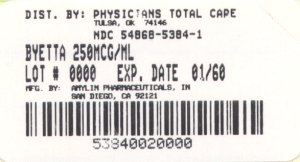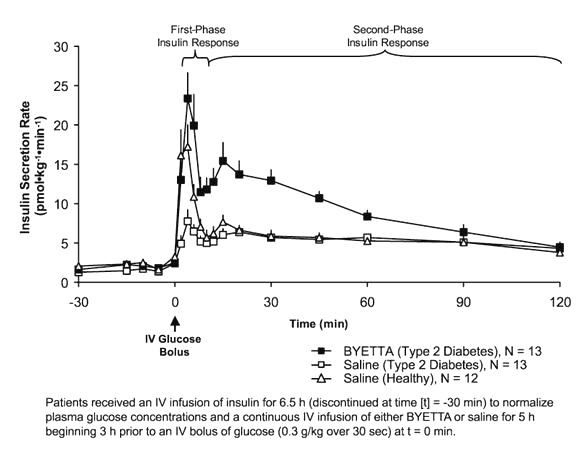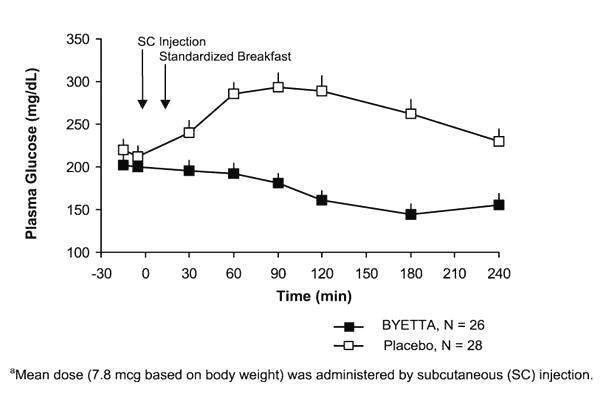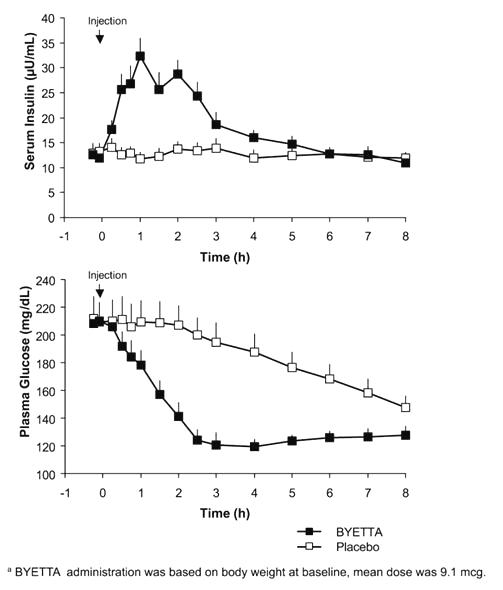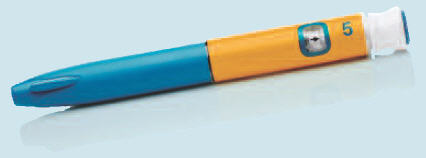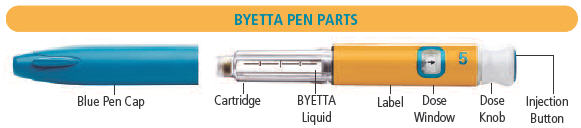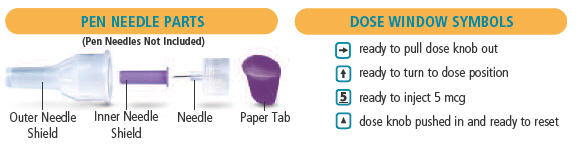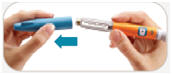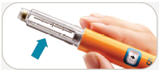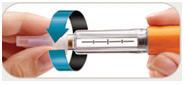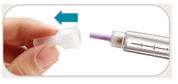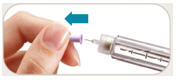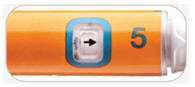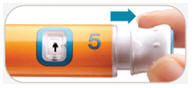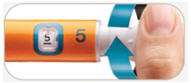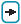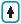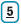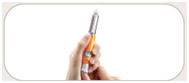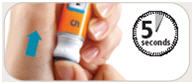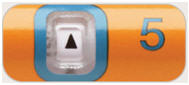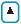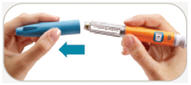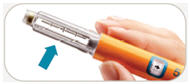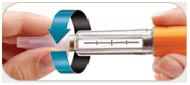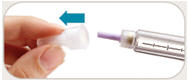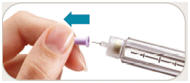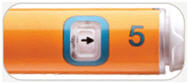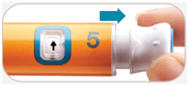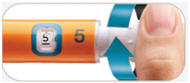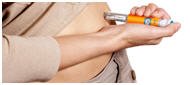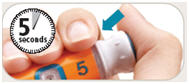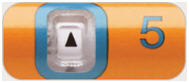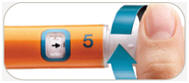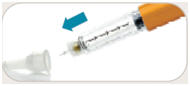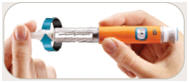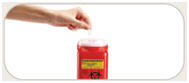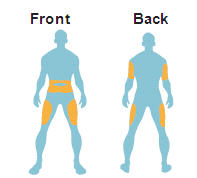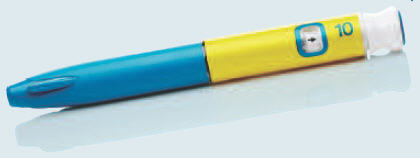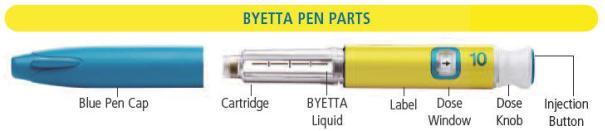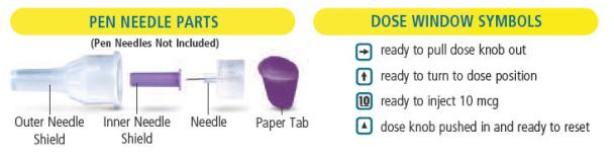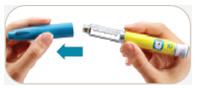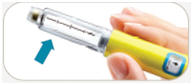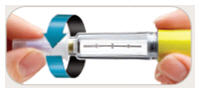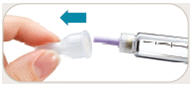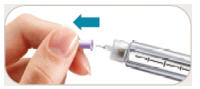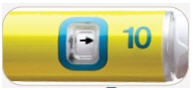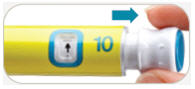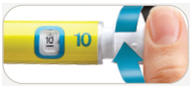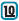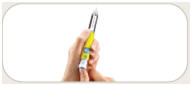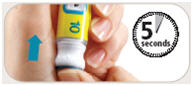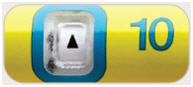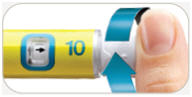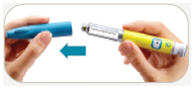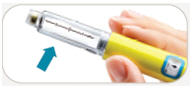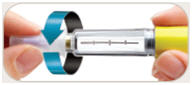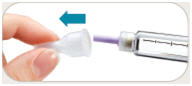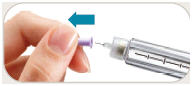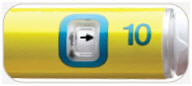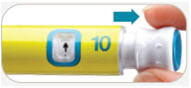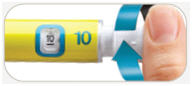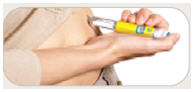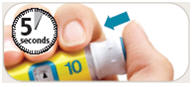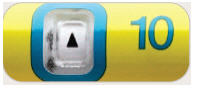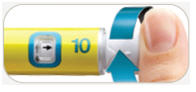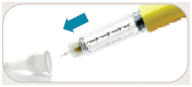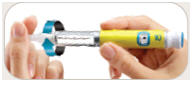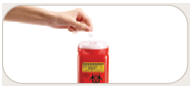 DRUG LABEL: BYETTA
NDC: 54868-5384 | Form: INJECTION
Manufacturer: Physicians Total Care, Inc.
Category: prescription | Type: HUMAN PRESCRIPTION DRUG LABEL
Date: 20120312

ACTIVE INGREDIENTS: exenatide 250 ug/1 mL
INACTIVE INGREDIENTS: metacresol 2.2 mg/1 mL; mannitol; acetic acid; sodium acetate; water

HIGHLIGHTS OF PRESCRIBING INFORMATION

These highlights do not include all the information needed to use BYETTA safely and effectively. See full prescribing information for BYETTA.
BYETTA® (exenatide) Injection
Initial U.S. Approval: 2005

RECENT MAJOR CHANGES

Dosage and Administration (2.1) | 10/2011
Warnings and Precautions, Use with Medications Known to Cause Hypoglycemia (5.2) | 10/2011

1 INDICATIONS AND USAGE

BYETTA is a glucagon-like peptide-1 (GLP-1) receptor agonist indicated as an adjunct to diet and exercise to improve glycemic control in adults with type 2 diabetes mellitus.

Important Limitations of Use

- Not a substitute for insulin. BYETTA should not be used for the treatment of type 1 diabetes or diabetic ketoacidosis (1.2).
- Concurrent use with prandial insulin has not been studied and cannot be recommended (1.2).
- Has not been studied in patients with a history of pancreatitis. Consider other antidiabetic therapies in patients with a history of pancreatitis (1.2).

2 DOSAGE AND ADMINISTRATION

- Inject subcutaneously within 60 minutes prior to morning and evening meals (or before the two main meals of the day, approximately 6 hours or more apart) (2.1).
- Initiate at 5 mcg per dose twice daily; increase to 10 mcg twice daily after 1 month based on clinical response (2.1).

3 DOSAGE FORMS AND STRENGTHS

BYETTA is supplied as 250 mcg/mL exenatide in:

- 5 mcg per dose, 60 doses, 1.2 mL prefilled pen
- 10 mcg per dose, 60 doses, 2.4 mL prefilled pen

4 CONTRAINDICATIONS

- History of severe hypersensitivity to exenatide or any product components (4.1).

5 WARNINGS AND PRECAUTIONS

- Pancreatitis: Postmarketing reports with exenatide, including fatal and non-fatal hemorrhagic or necrotizing pancreatitis. Discontinue BYETTA promptly. BYETTA should not be restarted. Consider other antidiabetic therapies in patients with a history of pancreatitis (5.1).
- Hypoglycemia: Increased risk when BYETTA is used in combination with medications known to cause hypoglycemia (e.g. insulin or insulin secretagogue). Consider reducing the dose of insulin or insulin secretagogue (5.2).
- Renal Impairment: Postmarketing reports with exenatide, sometimes requiring hemodialysis and kidney transplantation. BYETTA should not be used in patients with severe renal impairment or end-stage renal disease and should be used with caution in patients with renal transplantation. Caution should be applied when initiating BYETTA or escalating the dose of BYETTA in patients with moderate renal failure (5.3, 8.6, 12.3)
- Severe Gastrointestinal Disease: Use of BYETTA is not recommended in patients with severe gastrointestinal disease (e.g., gastroparesis) (5.4).
- Hypersensitivity: Postmarketing reports with exenatide of hypersensitivity reactions (e.g. anaphylaxis and angioedema). The patient should discontinue BYETTA and other suspect medications and promptly seek medical advice (5.6).
- Macrovascular outcomes: There have been no clinical studies establishing conclusive evidence of macrovascular risk reduction with BYETTA or any other antidiabetic drug (5.7).

6 ADVERSE REACTIONS

- Most common (≥5%) and occurring more frequently than placebo in clinical trials: nausea, hypoglycemia, vomiting, diarrhea, feeling jittery, dizziness, headache, dyspepsia, constipation, asthenia. Nausea usually decreases over time (5.2, 6).
- Postmarketing reports with exenatide of increased international normalized ratio (INR) with concomitant use of warfarin, sometimes with bleeding (6.2, 7.2).

To report SUSPECTED ADVERSE REACTIONS contact Amylin Pharmaceuticals, Inc. at 1-800-868-1190 and www.byetta.com or FDA at 1-800-FDA-1088 or www.fda.gov/medwatch

7 DRUG INTERACTIONS

- May impact absorption of orally administered medications (7.1, 12.3)
- Warfarin: Postmarketing reports of increased INR sometimes associated with bleeding. Monitor INR frequently until stable upon initiation or alteration of BYETTA therapy (6.2, 7.2).

8 USE IN SPECIFIC POPULATIONS

- Pregnancy: Based on animal data, BYETTA may cause fetal harm. BYETTA should be used during pregnancy only if the potential benefit justifies the potential risk to the fetus. To report drug exposure during pregnancy call 1-800-633-9081 (8.1).
- Nursing Mothers: Caution should be exercised when BYETTA is administered to a nursing woman (8.3).

FULL PRESCRIBING INFORMATION

1 INDICATIONS AND USAGE

1.1 Type 2 Diabetes Mellitus

BYETTA is indicated as an adjunct to diet and exercise to improve glycemic control in adults with type 2 diabetes mellitus.

1.2 Important Limitations of Use

BYETTA is not a substitute for insulin. BYETTA should not be used for the treatment of type 1 diabetes or diabetic ketoacidosis, as it would not be effective in these settings.

The concurrent use of BYETTA with prandial insulin has not been studied and cannot be recommended.

Based on postmarketing data BYETTA has been associated with acute pancreatitis, including fatal and non-fatal hemorrhagic or necrotizing pancreatitis. BYETTA has not been studied in patients with a history of pancreatitis. It is unknown whether patients with a history of pancreatitis are at increased risk for pancreatitis while using BYETTA. Other antidiabetic therapies should be considered in patients with a history of pancreatitis.

2 DOSAGE AND ADMINISTRATION

2.1 Recommended Dosing

BYETTA should be initiated at 5 mcg administered twice daily at any time within the 60-minute period before the morning and evening meals (or before the two main meals of the day, approximately 6 hours or more apart). BYETTA should not be administered after a meal. Based on clinical response, the dose of BYETTA can be increased to 10 mcg twice daily after 1 month of therapy. Initiation with 5 mcg reduces the incidence and severity of gastrointestinal side effects. Each dose should be administered as a subcutaneous (SC) injection in the thigh, abdomen, or upper arm. Do not mix BYETTA with insulin. Do not transfer BYETTA from the pen to a syringe or a vial. No data are available on the safety or efficacy of intravenous or intramuscular injection of BYETTA.

Use BYETTA only if it is clear, colorless and contains no particles.

3 DOSAGE FORMS AND STRENGTHS

BYETTA is supplied as a sterile solution for subcutaneous injection containing 250 mcg/mL exenatide in the following packages:

- 5 mcg per dose, 60 doses, 1.2 mL prefilled pen
- 10 mcg per dose, 60 doses, 2.4 mL prefilled pen

4 CONTRAINDICATIONS

4.1 Hypersensitivity

BYETTA is contraindicated in patients with prior severe hypersensitivity reactions to exenatide or to any of the product components.

5 WARNINGS AND PRECAUTIONS

5.1 Acute Pancreatitis

Based on postmarketing data BYETTA has been associated with acute pancreatitis, including fatal and non-fatal hemorrhagic or necrotizing pancreatitis. After initiation of BYETTA, and after dose increases, observe patients carefully for signs and symptoms of pancreatitis (including persistent severe abdominal pain, sometimes radiating to the back, which may or may not be accompanied by vomiting). If pancreatitis is suspected, BYETTA should promptly be discontinued and appropriate management should be initiated. If pancreatitis is confirmed, BYETTA should not be restarted. Consider antidiabetic therapies other than BYETTA in patients with a history of pancreatitis.

5.2 Use with Medications Known to Cause Hypoglycemia

The risk of hypoglycemia is increased when BYETTA is used in combination with a sulfonylurea. Therefore, patients receiving BYETTA and a sulfonylurea may require a lower dose of the sulfonylurea to reduce the risk of hypoglycemia.

When BYETTA is used in combination with insulin, the dose of insulin should be evaluated. In patients at increased risk of hypoglycemia consider reducing the dose of insulin [see Adverse Reactions (6.1)]. The concurrent use of BYETTA with prandial insulin has not been studied and cannot be recommended. It is also possible that the use of BYETTA with other glucose-independent insulin secretagogues (e.g. meglitinides) could increase the risk of hypoglycemia.

For additional information on glucose dependent effects see Mechanism of Action (12.1).

5.3 Renal Impairment

BYETTA should not be used in patients with severe renal impairment (creatinine clearance < 30 mL/min) or end-stage renal disease and should be used with caution in patients with renal transplantation [see Use in Specific Populations (8.6)]. In patients with end-stage renal disease receiving dialysis, single doses of BYETTA 5 mcg were not well-tolerated due to gastrointestinal side effects. Because BYETTA may induce nausea and vomiting with transient hypovolemia, treatment may worsen renal function. Caution should be applied when initiating or escalating doses of BYETTA from 5 mcg to 10 mcg in patients with moderate renal impairment (creatinine clearance 30 to 50 mL/min).

There have been postmarketing reports of altered renal function, including increased serum creatinine, renal impairment, worsened chronic renal failure and acute renal failure, sometimes requiring hemodialysis or kidney transplantation. Some of these events occurred in patients receiving one or more pharmacologic agents known to affect renal function or hydration status, such as angiotensin converting enzyme inhibitors, nonsteroidal anti-inflammatory drugs, or diuretics. Some events occurred in patients who had been experiencing nausea, vomiting, or diarrhea, with or without dehydration. Reversibility of altered renal function has been observed in many cases with supportive treatment and discontinuation of potentially causative agents, including BYETTA. Exenatide has not been found to be directly nephrotoxic in preclinical or clinical studies.

5.4 Gastrointestinal Disease

BYETTA has not been studied in patients with severe gastrointestinal disease, including gastroparesis. Because BYETTA is commonly associated with gastrointestinal adverse reactions, including nausea, vomiting, and diarrhea, the use of BYETTA is not recommended in patients with severe gastrointestinal disease.

5.5 Immunogenicity

Patients may develop antibodies to exenatide following treatment with BYETTA. Antibody levels were measured in 90% of subjects in the 30-week, 24-week and 16-week studies of BYETTA. In 3%, 4% and 1% of these patients, respectively, antibody formation was associated with an attenuated glycemic response. If there is worsening glycemic control or failure to achieve targeted glycemic control, alternative antidiabetic therapy should be considered [see Adverse Reactions (6.1)].

5.6 Hypersensitivity

There have been postmarketing reports of serious hypersensitivity reactions (e.g. anaphylaxis and angioedema) in patients treated with BYETTA. If a hypersensitivity reaction occurs, the patient should discontinue BYETTA and other suspect medications and promptly seek medical advice [see Adverse Reactions (6.2)].

5.7 Macrovascular Outcomes

There have been no clinical studies establishing conclusive evidence of macrovascular risk reduction with BYETTA or any other antidiabetic drug.

6 ADVERSE REACTIONS

6.1 Clinical Trial Experience

Because clinical trials are conducted under widely varying conditions, adverse reaction rates observed in the clinical trials of a drug cannot be directly compared to rates in the clinical trials of another drug and may not reflect the rates observed in practice.

Hypoglycemia

Table 1 summarizes the incidence and rate of hypoglycemia with BYETTA in six placebo-controlled clinical trials.

Table 1: Incidence (%) and Rate of Hypoglycemia When BYETTA was Used as Monotherapy or With Concomitant Antidiabetic Therapy in Six Placebo-Controlled Clinical Trials [A hypoglycemic episode was recorded if a patient reported symptoms of hypoglycemia with or without a blood glucose value consistent with hypoglycemia. Severe hypoglycemia was defined as an event with symptoms consistent with hypoglycemia requiring the assistance of another person and associated with either a blood glucose value consistent with hypoglycemia or prompt recovery after treatment for hypoglycemia.]
 | BYETTA
 | Placebo twice daily | 5 mcg twice daily | 10 mcg twice daily
Monotherapy (24 Weeks)
N | 77 | 77 | 78
% Overall | 1.3% | 5.2% | 3.8%
Rate (episodes/patient-year) | 0.03 | 0.21 | 0.52
% Severe | 0.0% | 0.0% | 0.0%
With Metformin (30 Weeks)
N | 113 | 110 | 113
% Overall | 5.3% | 4.5% | 5.3%
Rate (episodes/patient-year) | 0.12 | 0.13 | 0.12
% Severe | 0.0% | 0.0% | 0.0%
With a Sulfonylurea (30 Weeks)
N | 123 | 125 | 129
% Overall | 3.3% | 14.4% | 35.7%
Rate (episodes/patient-year) | 0.07 | 0.64 | 1.61
% Severe | 0.0% | 0.0% | 0.0%
With Metformin and a Sulfonylurea (30 Weeks)
N | 247 | 245 | 241
% Overall | 12.6% | 19.2% | 27.8%
Rate (episodes/patient-year) | 0.58 | 0.78 | 1.71
% Severe | 0.0% | 0.4% | 0.0%
With a Thiazolidinedione (16 Weeks)
N | 112 | not evaluated | 121
% Overall | 7.1% | not evaluated | 10.7%
Rate (episodes/patient-years) | 0.56 | not evaluated | 0.98
% Severe | 0.0% | not evaluated | 0.0%
With Insulin Glargine (30 Weeks) [When BYETTA was initiated in combination with insulin glargine, the dose of insulin glargine was decreased by 20% in patients with an HbA1c ≤ 8.0 % to minimize the risk of hypoglycemia. See Table 9 for insulin dose titration algorithm.]
N | 122 | not evaluated | 137
% Overall | 29.5% | not evaluated | 24.8%
Rate (episodes/patient-years) | 1.58 | not evaluated | 1.61
% Severe | 0.8% | not evaluated | 0.0%
N = The number of Intent-to-Treat subjects in each treatment group.

Immunogenicity

Antibodies were assessed in 90% of subjects in the 30-week, 24-week and 16-week studies of BYETTA. In the 30-week controlled trials of BYETTA add-on to metformin and/or sulfonylurea, antibodies were assessed at 2- to 6-week intervals. The mean antibody titer peaked at week 6 and was reduced by 55% by week 30. Three hundred and sixty patients (38%) had low titer antibodies (<625) to exenatide at 30 weeks. The level of glycemic control (HbA1c) in these patients was generally comparable to that observed in the 534 patients (56%) without antibody titers. An additional 59 patients (6%) had higher titer antibodies (≥625) at 30 weeks. Of these patients, 32 (3% overall) had an attenuated glycemic response to BYETTA; the remaining 27 (3% overall) had a glycemic response comparable to that of patients without antibodies [see Warnings and Precautions (5.5)].

In the 16-week trial of BYETTA add-on to thiazolidinediones, with or without metformin, 36 patients (31%) had low titer antibodies to exenatide at 16 weeks. The level of glycemic control in these patients was generally comparable to that observed in the 69 patients (60%) without antibody titer. An additional 10 patients (9%) had higher titer antibodies at 16 weeks. Of these patients, 4 (4% overall) had an attenuated glycemic response to BYETTA; the remaining 6 (5% overall) had a glycemic response comparable to that of patients without antibodies [see Warnings and Precautions (5.5)].

In the 24-week trial of BYETTA used as monotherapy, 40 patients (28%) had low titer antibodies to exenatide at 24 weeks. The level of glycemic control in these patients was generally comparable to that observed in the 101 patients (70%) without antibody titers. An additional 3 patients (2%) had higher titer antibodies at 24 weeks. Of these patients, 1 (1% overall) had an attenuated glycemic response to BYETTA; the remaining 2 (1% overall) had a glycemic response comparable to that of patients without antibodies [see Warnings and Precautions (5.5)].

Antibodies to exenatide were not assessed in the 30-week trial of BYETTA used in combination with insulin glargine.

Two hundred and ten patients with antibodies to exenatide in the BYETTA clinical trials were tested for the presence of cross-reactive antibodies to GLP-1 and/or glucagon. No treatment-emergent cross reactive antibodies were observed across the range of titers.

Other Adverse Reactions

Monotherapy

For the 24-week placebo-controlled study of BYETTA used as a monotherapy, Table 2 summarizes adverse reactions (excluding hypoglycemia) occurring with an incidence ≥2% and occurring more frequently in BYETTA-treated patients compared with placebo-treated patients.

Table 2: Treatment-Emergent Adverse Reactions ≥2% Incidence With BYETTA Used as Monotherapy (Excluding Hypoglycemia) [In a 24-week placebo-controlled trial.]
Monotherapy | Placebo BID N = 77 % | All BYETTA BID N = 155 %
Nausea | 0 | 8
Vomiting | 0 | 4
Dyspepsia | 0 | 3
BID = twice daily.

Adverse reactions reported in ≥1.0 to <2.0% of patients receiving BYETTA and reported more frequently than with placebo included decreased appetite, diarrhea, and dizziness. The most frequently reported adverse reaction associated with BYETTA, nausea, occurred in a dose-dependent fashion.

Two of the 155 patients treated with BYETTA withdrew due to adverse reactions of headache and nausea. No placebo-treated patients withdrew due to adverse reactions.

Combination Therapy

Add-on to metformin and/or sulfonylurea

In the three 30-week controlled trials of BYETTA add-on to metformin and/or sulfonylurea, adverse reactions (excluding hypoglycemia) with an incidence ≥2% and occurring more frequently in BYETTA-treated patients compared with placebo-treated patients [see Warnings and Precautions (5.2)] are summarized in Table 3.

Table 3: Treatment-Emergent Adverse Reactions ≥2% Incidence and Greater Incidence With BYETTA Treatment Used With Metformin and/or a Sulfonylurea (Excluding Hypoglycemia) [In three 30-week placebo-controlled clinical trials.]
 | Placebo BID N = 483 % | All BYETTA BID N = 963 %
Nausea | 18 | 44
Vomiting | 4 | 13
Diarrhea | 6 | 13
Feeling Jittery | 4 | 9
Dizziness | 6 | 9
Headache | 6 | 9
Dyspepsia | 3 | 6
Asthenia | 2 | 4
Gastroesophageal Reflux Disease | 1 | 3
Hyperhidrosis | 1 | 3
BID = twice daily.

Adverse reactions reported in ≥1.0 to <2.0% of patients receiving BYETTA and reported more frequently than with placebo included decreased appetite. Nausea was the most frequently reported adverse reaction and occurred in a dose-dependent fashion. With continued therapy, the frequency and severity decreased over time in most of the patients who initially experienced nausea. Patients in the long-term uncontrolled open-label extension studies at 52 weeks reported no new types of adverse reactions than those observed in the 30-week controlled trials.

The most common adverse reactions leading to withdrawal for BYETTA-treated patients were nausea (3% of patients) and vomiting (1%). For placebo-treated patients, <1% withdrew due to nausea and none due to vomiting.

Add-on to thiazolidinedione with or without metformin

For the 16-week placebo-controlled study of BYETTA add-on to a thiazolidinedione, with or without metformin, Table 4 summarizes the adverse reactions (excluding hypoglycemia) with an incidence of ≥2% and occurring more frequently in BYETTA-treated patients compared with placebo-treated patients.

Table 4: Treatment-Emergent Adverse Reactions ≥2% Incidence With BYETTA Used With a Thiazolidinedione, With or Without Metformin (Excluding Hypoglycemia) [In a 16-week placebo-controlled clinical trial.]
With a TZD or TZD/MET | Placebo N = 112 % | All BYETTA BID N = 121 %
Nausea | 15 | 40
Vomiting | 1 | 13
Dyspepsia | 1 | 7
Diarrhea | 3 | 6
Gastroesophageal Reflux Disease | 0 | 3
BID = twice daily.

Adverse reactions reported in ≥1.0 to <2.0% of patients receiving BYETTA and reported more frequently than with placebo included decreased appetite. Chills (n = 4) and injection-site reactions (n = 2) occurred only in BYETTA-treated patients. The two patients who reported an injection-site reaction had high titers of antibodies to exenatide. Two serious adverse events (chest pain and chronic hypersensitivity pneumonitis) were reported in the BYETTA arm. No serious adverse events were reported in the placebo arm.

The most common adverse reactions leading to withdrawal for BYETTA-treated patients were nausea (9%) and vomiting (5%). For placebo-treated patients, <1% withdrew due to nausea.

Add-on to insulin glargine with or without metformin and/or thiazolidinedione

For the 30-week placebo-controlled study of BYETTA as add-on to insulin glargine with or without oral antihyperglycemic medications, Table 5 summarizes adverse reactions (excluding hypoglycemia) occurring with an incidence ≥2% and occurring more frequently in BYETTA-treated patients compared with placebo-treated patients.

Table 5: Treatment-Emergent Adverse Reactions ≥2% Incidence With BYETTA Used With Insulin Glargine With or Without Oral Antihyperglycemic Medications (Excluding Hypoglycemia) [In a 30-week placebo-controlled clinical trial.]
With Insulin Glargine | Placebo N = 122 % | All BYETTA BID N = 137 %
Nausea | 8 | 41
Vomiting | 4 | 18
Diarrhea | 8 | 18
Headache | 4 | 14
Constipation | 2 | 10
Dyspepsia | 2 | 7
Asthenia | 1 | 5
Abdominal Distension | 1 | 4
Decreased Appetite | 0 | 3
Flatulence | 1 | 2
Gastroesophageal Reflux Disease | 1 | 2
BID = twice daily.

The most frequently reported adverse reactions leading to withdrawal for BYETTA-treated patients were nausea (5.1%) and vomiting (2.9%). No placebo-treated patients withdrew due to nausea or vomiting.

6.2 Post-Marketing Experience

The following additional adverse reactions have been reported during post-approval use of BYETTA. Because these events are reported voluntarily from a population of uncertain size, it is generally not possible to reliably estimate their frequency or establish a causal relationship to drug exposure.

Allergy/Hypersensitivity: injection-site reactions, generalized pruritus and/or urticaria, macular or papular rash, angioedema, anaphylactic reaction [see Warnings and Precautions (5.6)].

Drug Interactions: International normalized ratio (INR) increased with concomitant warfarin use sometimes associated with bleeding [see Drug Interactions (7.2)].

Gastrointestinal: nausea, vomiting, and/or diarrhea resulting in dehydration; abdominal distension, abdominal pain, eructation, constipation, flatulence, acute pancreatitis, hemorrhagic and necrotizing pancreatitis sometimes resulting in death [see Limitations of Use (1.2) and Warnings and Precautions (5.1)].

Neurologic: dysgeusia; somnolence

Renal and Urinary Disorders: altered renal function, including increased serum creatinine, renal impairment, worsened chronic renal failure or acute renal failure (sometimes requiring hemodialysis), kidney transplant and kidney transplant dysfunction [see Warnings and Precautions (5.3)].

Skin and Subcutaneous Tissue Disorders: alopecia

7 DRUG INTERACTIONS

7.1 Orally Administered Drugs

The effect of BYETTA to slow gastric emptying can reduce the extent and rate of absorption of orally administered drugs. BYETTA should be used with caution in patients receiving oral medications that have narrow therapeutic index or require rapid gastrointestinal absorption [see Adverse Reactions (6.2)]. For oral medications that are dependent on threshold concentrations for efficacy, such as contraceptives and antibiotics, patients should be advised to take those drugs at least 1 hour before BYETTA injection. If such drugs are to be administered with food, patients should be advised to take them with a meal or snack when BYETTA is not administered [see Clinical Pharmacology (12.3)].

7.2 Warfarin

There are postmarketing reports of increased INR sometimes associated with bleeding, with concomitant use of warfarin and BYETTA [see Adverse Reactions (6.2)]. In a drug interaction study, BYETTA did not have a significant effect on INR [see Clinical Pharmacology (12.3)]. In patients taking warfarin, prothrombin time should be monitored more frequently after initiation or alteration of BYETTA therapy. Once a stable prothrombin time has been documented, prothrombin times can be monitored at the intervals usually recommended for patients on warfarin.

8 USE IN SPECIFIC POPULATIONS

8.1 Pregnancy

TERATOGENIC EFFECTS

Pregnancy Category C

There are no adequate and well-controlled studies of BYETTA use in pregnant women. In animal studies, exenatide caused cleft palate, irregular skeletal ossification and an increased number of neonatal deaths. BYETTA should be used during pregnancy only if the potential benefit justifies the potential risk to the fetus.

Female mice given SC doses of 6, 68, or 760 mcg/kg/day beginning 2 weeks prior to and throughout mating until gestation day 7 had no adverse fetal effects. At the maximal dose, 760 mcg/kg/day, systemic exposures were up to 390 times the human exposure resulting from the maximum recommended dose of 20 mcg/day, based on AUC [see Nonclinical Toxicology (13.3)].

In developmental toxicity studies, pregnant animals received exenatide subcutaneously during organogenesis. Specifically, fetuses from pregnant rabbits given SC doses of 0.2, 2, 22, 156, or 260 mcg/kg/day from gestation day 6 through 18 experienced irregular skeletal ossifications from exposures 12 times the human exposure resulting from the maximum recommended dose of 20 mcg/day, based on AUC. Moreover, fetuses from pregnant mice given SC doses of 6, 68, 460, or 760 mcg/kg/day from gestation day 6 through 15 demonstrated reduced fetal and neonatal growth, cleft palate and skeletal effects at systemic exposure 3 times the human exposure resulting from the maximum recommended dose of 20 mcg/day, based on AUC [see Nonclinical Toxicology (13.3)].

Lactating mice given SC doses of 6, 68, or 760 mcg/kg/day from gestation day 6 through lactation day 20 (weaning), experienced an increased number of neonatal deaths. Deaths were observed on postpartum days 2-4 in dams given 6 mcg/kg/day, a systemic exposure 3 times the human exposure resulting from the maximum recommended dose of 20 mcg/day, based on AUC [see Nonclinical Toxicology (13.3)].

Pregnancy Registry

Amylin Pharmaceuticals, Inc. maintains a Pregnancy Registry to monitor pregnancy outcomes of women exposed to exenatide during pregnancy. Physicians are encouraged to register patients by calling 1-800-633-9081.

8.3 Nursing Mothers

It is not known whether exenatide is excreted in human milk. However, exenatide is present at low concentrations (less than or equal to 2.5% of the concentration in maternal plasma following subcutaneous dosing) in the milk of lactating mice. Many drugs are excreted in human milk and because of the potential for clinically significant adverse reactions in nursing infants from exenatide, a decision should be made whether to discontinue nursing or discontinue the drug, taking into account these potential risks against the glycemic benefits to the lactating woman. Caution should be exercised when BYETTA is administered to a nursing woman.

8.4 Pediatric Use

Safety and effectiveness of BYETTA have not been established in pediatric patients.

8.5 Geriatric Use

Population pharmacokinetic analysis of patients ranging from 22 to 73 years of age suggests that age does not influence the pharmacokinetic properties of exenatide [see Clinical Pharmacology (12.3)]. BYETTA was studied in 282 patients 65 years of age or older and in 16 patients 75 years of age or older. No differences in safety or effectiveness were observed between these patients and younger patients. Because elderly patients are more likely to have decreased renal function, care should be taken in dose selection in the elderly based on renal function.

8.6 Renal Impairment

BYETTA is not recommended for use in patients with end-stage renal disease or severe renal impairment (creatinine clearance < 30 mL/min) and should be used with caution in patients with renal transplantation. No dosage adjustment of BYETTA is required in patients with mild renal impairment (creatinine clearance 50 to 80 mL/min). Caution should be applied when initiating or escalating doses of BYETTA from 5 mcg to 10 mcg in patients with moderate renal impairment (creatinine clearance 30 to 50 mL/min) [see Clinical Pharmacology (12.3)].

8.7 Hepatic Impairment

No pharmacokinetic study has been performed in patients with a diagnosis of acute or chronic hepatic impairment. Because exenatide is cleared primarily by the kidney, hepatic dysfunction is not expected to affect blood concentrations of exenatide [see Clinical Pharmacology (12.3)].

10 OVERDOSAGE

In a clinical study of BYETTA, three patients with type 2 diabetes each experienced a single overdose of 100 mcg SC (10 times the maximum recommended dose). Effects of the overdoses included severe nausea, severe vomiting, and rapidly declining blood glucose concentrations. One of the three patients experienced severe hypoglycemia requiring parenteral glucose administration. The three patients recovered without complication. In the event of overdose, appropriate supportive treatment should be initiated according to the patient's clinical signs and symptoms.

11 DESCRIPTION

BYETTA (exenatide) is a synthetic peptide that was originally identified in the lizard Heloderma suspectum. Exenatide differs in chemical structure and pharmacological action from insulin, sulfonylureas (including D-phenylalanine derivatives and meglitinides), biguanides, thiazolidinediones, alpha-glucosidase inhibitors, amylinomimetics and dipeptidyl peptidase-4 inhibitors.

Exenatide is a 39-amino acid peptide amide. Exenatide has the empirical formula C184H282N50O60S and molecular weight of 4186.6 Daltons. The amino acid sequence for exenatide is shown below.

H-His-Gly-Glu-Gly-Thr-Phe-Thr-Ser-Asp-Leu-Ser-Lys-Gln-Met-Glu-Glu-Glu-Ala-Val-Arg-Leu-Phe-Ile-Glu-Trp-Leu-Lys-Asn-Gly-Gly-Pro-Ser-Ser-Gly-Ala-Pro-Pro-Pro-Ser-NH2

BYETTA is supplied for SC injection as a sterile, preserved isotonic solution in a glass cartridge that has been assembled in a pen-injector (pen). Each milliliter (mL) contains 250 micrograms (mcg) synthetic exenatide, 2.2 mg metacresol as an antimicrobial preservative, mannitol as a tonicity-adjusting agent, and glacial acetic acid and sodium acetate trihydrate in water for injection as a buffering solution at pH 4.5. Two prefilled pens are available to deliver unit doses of 5 mcg or 10 mcg. Each prefilled pen will deliver 60 doses to provide for 30 days of twice daily administration (BID).

12 CLINICAL PHARMACOLOGY

12.1 Mechanism of Action

Incretins, such as glucagon-like peptide-1 (GLP-1), enhance glucose-dependent insulin secretion and exhibit other antihyperglycemic actions following their release into the circulation from the gut. BYETTA is a GLP-1 receptor agonist that enhances glucose-dependent insulin secretion by the pancreatic beta-cell, suppresses inappropriately elevated glucagon secretion, and slows gastric emptying.

The amino acid sequence of exenatide partially overlaps that of human GLP-1. Exenatide has been shown to bind and activate the human GLP-1 receptor in vitro. This leads to an increase in both glucose-dependent synthesis of insulin, and in vivo secretion of insulin from pancreatic beta cells, by mechanisms involving cyclic AMP and/or other intracellular signaling pathways.

BYETTA improves glycemic control by reducing fasting and postprandial glucose concentrations in patients with type 2 diabetes through the actions described below.

12.2 Pharmacodynamics

Glucose-dependent insulin secretion: BYETTA has acute effects on pancreatic beta-cell responsiveness to glucose leading to insulin release predominantly in the presence of elevated glucose concentrations. This insulin secretion subsides as blood glucose concentrations decrease and approach euglycemia. However, BYETTA does not impair the normal glucagon response to hypoglycemia.

First-phase insulin response: In healthy individuals, robust insulin secretion occurs during the first 10 minutes following intravenous (IV) glucose administration. This secretion, known as the "first-phase insulin response," is characteristically absent in patients with type 2 diabetes. The loss of the first-phase insulin response is an early beta-cell defect in type 2 diabetes. Administration of BYETTA at therapeutic plasma concentrations restored first-phase insulin response to an IV bolus of glucose in patients with type 2 diabetes (Figure 1). Both first-phase insulin secretion and second-phase insulin secretion were significantly increased in patients with type 2 diabetes treated with BYETTA compared with saline (p <0.001 for both).

Figure 1: Mean (+SEM) Insulin Secretion Rate During Infusion of BYETTA or Saline in Patients With Type 2 Diabetes and During Infusion of Saline in Healthy Subjects

Glucagon secretion: In patients with type 2 diabetes, BYETTA moderates glucagon secretion and lowers serum glucagon concentrations during periods of hyperglycemia. Lower glucagon concentrations lead to decreased hepatic glucose output and decreased insulin demand.

Gastric emptying: BYETTA slows gastric emptying, thereby reducing the rate at which meal-derived glucose appears in the circulation.

Food intake: In both animals and humans, administration of exenatide has been shown to reduce food intake.

Postprandial Glucose

In patients with type 2 diabetes, BYETTA reduces postprandial plasma glucose concentrations (Figure 2).

Figure 2: Mean (+SEM) Postprandial Plasma Glucose Concentrations on Day 1 of BYETTAa Treatment in Patients With Type 2 Diabetes Treated With Metformin, a Sulfonylurea, or Both (N = 54)

Fasting Glucose

In a single-dose crossover study in patients with type 2 diabetes and fasting hyperglycemia, immediate insulin release followed injection of BYETTA. Plasma glucose concentrations were significantly reduced with BYETTA compared with placebo (Figure 3).

Figure 3: Mean (+SEM) Serum Insulin and Plasma Glucose Concentrations Following a One-Time Injection of BYETTAa or Placebo in Fasting Patients With Type 2 Diabetes (N = 12)

Cardiac Electrophysiology

The effect of exenatide 10 µg subcutaneously on QTc interval was evaluated in a randomized, placebo-, and active-controlled (moxifloxacin 400 mg) crossover thorough QTc study in 62 healthy subjects. In this study with demonstrated ability to detect small effects, the upper bound of the 90% confidence interval for the largest placebo-adjusted, baseline-corrected QTc was below 10 ms. Thus, BYETTA (10 mcg single dose) was not associated with clinically meaningful prolongation of the QTc interval.

12.3 Pharmacokinetics

Absorption

Following SC administration to patients with type 2 diabetes, exenatide reaches median peak plasma concentrations in 2.1 h. The mean peak exenatide concentration (Cmax) was 211 pg/mL and overall mean area under the time-concentration curve (AUC0-inf) was 1036 pg∙h/mL following SC administration of a 10-mcg dose of BYETTA. Exenatide exposure (AUC) increased proportionally over the therapeutic dose range of 5 mcg to 10 mcg. The Cmax values increased less than proportionally over the same range. Similar exposure is achieved with SC administration of BYETTA in the abdomen, thigh, or upper arm.

Distribution

The mean apparent volume of distribution of exenatide following SC administration of a single dose of BYETTA is 28.3 L.

Metabolism and Elimination

Nonclinical studies have shown that exenatide is predominantly eliminated by glomerular filtration with subsequent proteolytic degradation. The mean apparent clearance of exenatide in humans is 9.1 L/h and the mean terminal half-life is 2.4 h. These pharmacokinetic characteristics of exenatide are independent of the dose. In most individuals, exenatide concentrations are measurable for approximately 10 h post-dose.

Drug Interactions

Acetaminophen

When 1000 mg acetaminophen elixir was given with 10 mcg BYETTA (0 h) and 1 hour, 2 hours, and 4 hours after BYETTA injection, acetaminophen AUCs were decreased by 21%, 23%, 24%, and 14%, respectively; Cmax was decreased by 37%, 56%, 54%, and 41%, respectively; Tmax was increased from 0.6 hour in the control period to 0.9 hour, 4.2 hours, 3.3 hours, and 1.6 hours, respectively. Acetaminophen AUC, Cmax and Tmax were not significantly changed when acetaminophen was given 1 hour before BYETTA injection.

Digoxin

Administration of repeated doses of BYETTA (10 mcg BID) 30 minutes before oral digoxin (0.25 mg QD) decreased the Cmax of digoxin by 17% and delayed the Tmax of digoxin by approximately 2.5 hours; however, the overall steady-state pharmacokinetic exposure (e.g., AUC) of digoxin was not changed.

Lovastatin

Administration of BYETTA (10 mcg BID) 30 minutes before a single oral dose of lovastatin (40 mg) decreased the AUC and Cmax of lovastatin by approximately 40% and 28%, respectively, and delayed the Tmax by about 4 hours compared with lovastatin administered alone. In the 30-week controlled clinical trials of BYETTA, the use of BYETTA in patients already receiving HMG CoA reductase inhibitors was not associated with consistent changes in lipid profiles compared to baseline.

Lisinopril

In patients with mild to moderate hypertension stabilized on lisinopril (5 to 20 mg/day), BYETTA (10 mcg BID) did not alter steady-state Cmax or AUC of lisinopril. Lisinopril steady-state Tmax was delayed by 2 hours. There were no changes in 24-h mean systolic and diastolic blood pressure.

Oral Contraceptives

The effect of BYETTA (10 mcg BID) on single and on multiple doses of a combination oral contraceptive (30 mcg ethinyl estradiol plus 150 mcg levonorgestrel) was studied in healthy female subjects. Repeated daily doses of the oral contraceptive (OC) given 30 minutes after BYETTA administration decreased the Cmax of ethinyl estradiol and levonorgestrel by 45% and 27%, respectively and delayed the Tmax of ethinyl estradiol and levonorgestrel by 3.0 hours and 3.5 hours, respectively, as compared to the oral contraceptive administered alone. Administration of repeated daily doses of the OC one hour prior to BYETTA administration decreased the mean Cmax of ethinyl estradiol by 15% but the mean Cmax of levonorgestrel was not significantly changed as compared to when the OC was given alone. BYETTA did not alter the mean trough concentrations of levonorgestrel after repeated daily dosing of the oral contraceptive for both regimens. However, the mean trough concentration of ethinyl estradiol was increased by 20% when the OC was administered 30 minutes after BYETTA administration injection as compared to when the OC was given alone. The effect of BYETTA on OC pharmacokinetics is confounded by the possible food effect on OC in this study. Therefore, OC products should be administered at least one hour prior to BYETTA injection.

Warfarin

Administration of warfarin (25 mg) 35 minutes after repeated doses of BYETTA (5 mcg BID on days 1-2 and 10 mcg BID on days 3-9) in healthy volunteers delayed warfarin Tmax by approximately 2 hours. No clinically relevant effects on Cmax or AUC of S- and R-enantiomers of warfarin were observed. BYETTA did not significantly alter the pharmacodynamic properties (e.g., international normalized ratio) of warfarin [see Drug Interactions (7.2)].

Specific Populations

Renal Impairment

Pharmacokinetics of exenatide was studied in subjects with normal, mild, or moderate renal impairment and subjects with end stage renal disease. In subjects with mild to moderate renal impairment (creatinine clearance 30 to 80 mL/min), exenatide exposure was similar to that of subjects with normal renal function. However, in subjects with end-stage renal disease receiving dialysis, mean exenatide exposure increased by 3.37-fold compared to that of subjects with normal renal function. [see Use in Specific Populations (8.6)].

Hepatic Impairment

No pharmacokinetic study has been performed in patients with a diagnosis of acute or chronic hepatic impairment [see Use in Specific Populations (8.7)].

Age

Population pharmacokinetic analysis of patients ranging from 22 to 73 years of age suggests that age does not influence the pharmacokinetic properties of exenatide [see Use in Specific Population (8.5)].

Gender

Population pharmacokinetic analysis of male and female patients suggests that gender does not influence the distribution and elimination of exenatide.

Race

Population pharmacokinetic analysis of samples from Caucasian, Hispanic, Asian, and Black patients suggests that race has no significant influence on the pharmacokinetics of exenatide.

Body Mass Index

Population pharmacokinetic analysis of patients with body mass indices (BMI) ≥30 kg/m^2 and <30 kg/m^2 suggests that BMI has no significant effect on the pharmacokinetics of exenatide.

13 NONCLINICAL TOXICOLOGY

13.1 Carcinogenesis, Mutagenesis, Impairment of Fertility

A 104-week carcinogenicity study was conducted in male and female rats at doses of 18, 70, or 250 mcg/kg/day administered by bolus SC injection. Benign thyroid C-cell adenomas were observed in female rats at all exenatide doses. The incidences in female rats were 8% and 5% in the two control groups and 14%, 11%, and 23% in the low-, medium-, and high-dose groups with systemic exposures of 5, 22, and 130 times, respectively, the human exposure resulting from the maximum recommended dose of 20 mcg/day, based on plasma area under the curve (AUC).

In a 104-week carcinogenicity study in mice at doses of 18, 70, or 250 mcg/kg/day administered by bolus SC injection, no evidence of tumors was observed at doses up to 250 mcg/kg/day, a systemic exposure up to 95 times the human exposure resulting from the maximum recommended dose of 20 mcg/day, based on AUC.

Exenatide was not mutagenic or clastogenic, with or without metabolic activation, in the Ames bacterial mutagenicity assay or chromosomal aberration assay in Chinese hamster ovary cells. Exenatide was negative in the in vivo mouse micronucleus assay.

In mouse fertility studies with SC doses of 6, 68 or 760 mcg/kg/day, males were treated for 4 weeks prior to and throughout mating, and females were treated 2 weeks prior to mating and throughout mating until gestation day 7. No adverse effect on fertility was observed at 760 mcg/kg/day, a systemic exposure 390 times the human exposure resulting from the maximum recommended dose of 20 mcg/day, based on AUC.

13.3 Reproductive and Developmental Toxicology

In female mice given SC doses of 6, 68, or 760 mcg/kg/day beginning 2 weeks prior to and throughout mating until gestation day 7, there were no adverse fetal effects at doses up to 760 mcg/kg/day, systemic exposures up to 390 times the human exposure resulting from the maximum recommended dose of 20 mcg/day, based on AUC.

In pregnant mice given SC doses of 6, 68, 460, or 760 mcg/kg/day from gestation day 6 through 15 (organogenesis), cleft palate (some with holes) and irregular fetal skeletal ossification of rib and skull bones were observed at 6 mcg/kg/day, a systemic exposure 3 times the human exposure resulting from the maximum recommended dose of 20 mcg/day, based on AUC.

In pregnant rabbits given SC doses of 0.2, 2, 22, 156, or 260 mcg/kg/day from gestation day 6 through 18 (organogenesis), irregular fetal skeletal ossifications were observed at 2 mcg/kg/day, a systemic exposure 12 times the human exposure resulting from the maximum recommended dose of 20 mcg/day, based on AUC.

In pregnant mice given SC doses of 6, 68, or 760 mcg/kg/day from gestation day 6 through lactation day 20 (weaning), an increased number of neonatal deaths was observed on postpartum days 2-4 in dams given 6 mcg/kg/day, a systemic exposure 3 times the human exposure resulting from the maximum recommended dose of 20 mcg/day, based on AUC.

14 CLINICAL STUDIES

BYETTA has been studied as monotherapy and in combination with metformin, a sulfonylurea, a thiazolidinedione, a combination of metformin and a sulfonylurea, a combination of metformin and a thiazolidinedione, or in combination with insulin glargine with or without metformin and/or thiazolidinedione.

14.1 Monotherapy

In a randomized, double-blind, placebo-controlled trial of 24 weeks duration, BYETTA 5 mcg BID (n = 77), BYETTA 10 mcg BID (n = 78), or placebo BID (n = 77) was used as monotherapy in patients with entry HbA1c ranging from 6.5-10%. All patients assigned to BYETTA initially received 5 mcg BID for 4 weeks. After 4 weeks, those patients either continued to receive BYETTA 5 mcg BID or had their dose increased to 10 mcg BID. Patients assigned to placebo received placebo BID throughout the trial. BYETTA or placebo was injected subcutaneously before the morning and evening meals. The majority of patients (68%) were Caucasian, 26% were West Asian, 3% were Hispanic, 3% were Black, and 0.4% were East Asian.

The primary endpoint was the change in HbA1c from baseline to Week 24 (or the last value at time of early discontinuation). Compared to placebo, BYETTA 5 mcg BID and 10 mcg BID resulted in statistically significant reductions in HbA1c from baseline at Week 24 (Table 6).

Table 6: Results of 24-Week Placebo-Controlled Trial of BYETTA Used as Monotherapy
 | Placebo BID | BYETTA 5 mcg BID | BYETTA 10 mcg [BYETTA 5 mcg twice daily (BID) for 1 month followed by 10 mcg BID for 5 months before the morning and evening meals.] BID
Intent-to-Treat Population (N) | 77 | 77 | 78
HbA1c (%), Mean
Baseline | 7.8 | 7.9 | 7.8
Change at Week 24 [Least squares means are adjusted for screening HbA1c strata and baseline value of the dependent variable.] | -0.2 | -0.7 | -0.9
Difference from placebo(95% CI) |  | -0.5 [-0.9, -0.2] [p <0.01, treatment vs. placebo.] | -0.7 [-1.0, -0.3]
Proportion Achieving HbA1c <7% | 38% | 48% | 53%
Body Weight (kg), Mean
Baseline | 86.1 | 85.1 | 86.2
Change at Week 24 | -1.5 | -2.7 | -2.9
Difference from placebo(95% CI) |  | -1.3 [-2.3, -0.2] | -1.5 [-2.5, -0.4]
Fasting Serum Glucose [Measured using the hexokinase-based glucose method.] (mg/dL), Mean
Baseline | 159 | 166 | 155
Change at Week 24 | -5 | -17 | -19
Difference from placebo (95% CI) |  | -12 [-23.2, -1.3] | -14 [-24.5, -2.5]
BID = twice daily.

On average, there were no adverse effects of exenatide on blood pressure or lipids.

14.2 Combination Therapy With Oral Antihyperglycemic Medicines

Three 30-week, double-blind, placebo-controlled trials were conducted to evaluate the safety and efficacy of BYETTA in patients with type 2 diabetes whose glycemic control was inadequate with metformin alone, a sulfonylurea alone, or metformin in combination with a sulfonylurea. In addition, a 16-week, placebo-controlled trial was conducted where BYETTA was added to existing thiazolidinedione (pioglitazone or rosiglitazone) treatment, with or without metformin, in patients with type 2 diabetes with inadequate glycemic control.

In the 30-week trials, after a 4-week placebo lead-in period, patients were randomly assigned to receive BYETTA 5 mcg BID, BYETTA 10 mcg BID, or placebo BID before the morning and evening meals, in addition to their existing oral antidiabetic agent. All patients assigned to BYETTA initially received 5 mcg BID for 4 weeks. After 4 weeks, those patients either continued to receive BYETTA 5 mcg BID or had their dose increased to 10 mcg BID. Patients assigned to placebo received placebo BID throughout the study. A total of 1446 patients were randomized in the three 30-week trials: 991 (69%) were Caucasian, 224 (16%) were Hispanic, and 174 (12%) were Black. Mean HbA1c values at baseline for the trials ranged from 8.2% to 8.7%.

In the placebo-controlled trial of 16 weeks duration, BYETTA (n = 121) or placebo (n = 112) was added to existing thiazolidinedione (pioglitazone or rosiglitazone) treatment, with or without metformin. Randomization to BYETTA or placebo was stratified based on whether the patients were receiving metformin. BYETTA treatment was initiated at a dose of 5 mcg BID for 4 weeks then increased to 10 mcg BID for 12 more weeks. Patients assigned to placebo received placebo BID throughout the study. BYETTA or placebo was injected subcutaneously before the morning and evening meals. In this trial, 79% of patients were taking a thiazolidinedione and metformin and 21% were taking a thiazolidinedione alone. The majority of patients (84%) were Caucasian, 8% were Hispanic and 3% were Black. The mean baseline HbA1c values were 7.9% for BYETTA and placebo.

The primary endpoint in each study was the mean change in HbA1c from baseline to study end (or early discontinuation). Table 7 summarizes the study results for the 30-week and 16-week clinical trials.

Table 7: Results of 30-Week and 16-Week Placebo-Controlled Trials of BYETTA Used in Combination with Oral Antidiabetic Agents
 | Placebo BID | BYETTA 5 mcg BID | BYETTA 10 mcg BID
 | In Combination With Metformin (30 Weeks)
Intent-to-Treat Population (N) | 113 | 110 | 113
HbA1c (%), Mean
Baseline | 8.2 | 8.3 | 8.2
Change at Week 30 [Least squares means are adjusted for baseline HbA1c strata or value, investigator site, baseline value of the dependent variable (if applicable), and background antihyperglycemic therapy (if applicable).] | -0.0 | -0.5 | -0.9
Difference from placebo (95% CI) |  | -0.5 [-0.7, -0.2] [p <0.01, treatment vs. placebo.] | -0.9 [-1.1, -0.6]
Proportion Achieving HbA1c <7% | 12% | 32% | 40%
Body Weight (kg), Mean
Baseline | 99.9 | 100.0 | 100.9
Change at Week 30 | -0.2 | -1.3 | -2.6
Difference from placebo (95% CI) |  | -1.1 [-2.2, -0.0] | -2.4 [-3.5, -1.3]
Fasting Plasma Glucose [Measured using the hexokinase-based glucose method.] (mg/dL), Mean
Baseline | 169 | 176 | 168
Change at Week 30 | +14 | -5 | -10
Difference from placebo (95% CI) |  | -20 [-32, -7] | -24 [-37, -12]
 | In Combination With a Sulfonylurea (30 Weeks)
Intent-to-Treat Population (N) | 123 | 125 | 129
HbA1c (%), Mean
Baseline | 8.7 | 8.5 | 8.6
Change at Week 30 | +0.1 | -0.5 | -0.9
Difference from placebo (95% CI) |  | -0.6 [-0.9, -0.3] | -1.0 [-1.3, -0.7]
Proportion Achieving HbA1c <7% | 10% | 25% | 36%
Body Weight (kg), Mean
Baseline | 99.1 | 94.9 | 95.2
Change at Week 30 | -0.8 | -1.1 | -1.6
Difference from placebo (95% CI) |  | -0.3 [-1.1, 0.6] | -0.9 [-1.7, -0.0]
Fasting Plasma Glucose (mg/dL), Mean
Baseline | 194 | 180 | 178
Change at Week 30 | +6 | -5 | -11
Difference from placebo (95% CI) |  | -11 [-25, 3] | -17 [-30, -3]
 | In Combination With Metformin and a Sulfonylurea (30 Weeks)
Intent-to-Treat Population (N) | 247 | 245 | 241
HbA1c (%), Mean
Baseline | 8.5 | 8.5 | 8.5
Change at Week 30 | +0.1 | -0.7 | -0.9
Difference from placebo (95% CI) |  | -0.8 [-1.0, -0.6] | -1.0 [-1.2, -0.8]
Proportion Achieving HbA1c <7% | 8% | 25% | 31%
Body Weight (kg), Mean
Baseline | 99.1 | 96.9 | 98.4
Change at Week 30 | -0.9 | -1.6 | -1.6
Difference from placebo (95% CI) |  | -0.7 [-1.2, -0.2] | -0.7 [-1.3, -0.2]
Fasting Plasma Glucose (mg/dL), Mean
Baseline | 181 | 182 | 178
Change at Week 30 | +13 | -11 | -12
Difference from placebo (95% CI) |  | -24 [-33, -15] | -25 [-34, -16]
 | In Combination With a Thiazolidinedione or a Thiazolidinedione plus Metformin (16 Weeks)
Intent-to-Treat Population (N) | 112 | Dose not studied | 121
HbA1c (%), Mean
Baseline | 7.9 | Dose not studied | 7.9
Change at Week 16 | +0.1 | Dose not studied | -0.7
Difference from placebo (95% CI) |  | Dose not studied | -0.9 [-1.1, -0.7]
Proportion Achieving HbA1c <7% | 15% | Dose not studied | 51%
Body Weight (kg), Mean
Baseline | 96.8 | Dose not studied | 97.5
Change at Week 16 | -0.0 | Dose not studied | -1.5
Difference from placebo (95% CI) |  | Dose not studied | -1.5 [-2.2, -0.7]
Fasting Serum Glucose (mg/dL), Mean
Baseline | 159 | Dose not studied | 164
Change at Week 16 | +4 | Dose not studied | -21
Difference from placebo (95% CI) |  | Dose not studied | -25 [-33, -16]
BID = twice daily.

HbA1c

The addition of BYETTA to a regimen of metformin, a sulfonylurea, or both, resulted in statistically significant reductions from baseline in HbA1c compared with patients receiving placebo added to these agents in the three controlled trials (Table 7).

In the 16-week trial of BYETTA add-on to thiazolidinediones, with or without metformin, BYETTA resulted in statistically significant reductions from baseline in HbA1c compared with patients receiving placebo (Table 7).

Postprandial Glucose

Postprandial glucose was measured after a mixed meal tolerance test in 9.5% of patients participating in the 30-week add-on to metformin, add-on to sulfonylurea, and add-on to metformin in combination with sulfonylurea clinical trials. In this pooled subset of patients, BYETTA reduced postprandial plasma glucose concentrations in a dose-dependent manner. The mean (SD) change in 2-h postprandial glucose concentration following administration of BYETTA at Week 30 relative to baseline was -63 (65) mg/dL for 5 mcg BID (n = 42), -71 (73) mg/dL for 10 mcg BID (n = 52), and +11 (69) mg/dL for placebo BID (n = 44).

14.3 Combination with Insulin Glargine

A 30-week, double-blind, placebo-controlled trial was conducted to evaluate the efficacy and safety of BYETTA (n = 137) versus placebo (n = 122) when added to titrated insulin glargine, with or without metformin and/or thiazolidinedione, in patients with type 2 diabetes with inadequate glycemic control.

All patients assigned to BYETTA initially received 5 mcg BID for 4 weeks. After 4 weeks, those patients assigned to BYETTA had their dose increased to 10 mcg BID. Patients assigned to placebo received placebo BID throughout the trial. BYETTA or placebo was injected subcutaneously before the morning and evening meals. Patients with an HbA1c ≤8.0% decreased their prestudy dose of insulin glargine by 20% and patients with an HbA1c ≥8.1% maintained their current dose of insulin glargine. Five weeks after initiating randomized treatment, insulin doses were titrated with guidance from the investigator toward predefined fasting glucose targets according to the dose titration algorithm provided in Table 9. The majority of patients (78%) were Caucasian, 10% were American Indian or Alaska Native, 9% were Black, 3% were Asian, and 0.8% were of multiple origins.

The primary endpoint was the change in HbA1c from baseline to Week 30. Compared to placebo, BYETTA 10 mcg BID resulted in statistically significant reductions in HbA1c from baseline at Week 30 (Table 8) in patients receiving titrated insulin glargine.

Table 8: 30-Week Placebo-Controlled Trial of BYETTA Used in Combination with Insulin Glargine With or Without Metformin and/or Thiazolidinediones
 | Placebo BID + Titrated Insulin Glargine | BYETTA 10 mcg [BYETTA 5 mcg twice daily for 1 month followed by 10 mcg BID for 5 months for the 30-week trial.] BID + Titrated Insulin Glargine
Intent-to-Treat Population (N) | 122 | 137
HbA1c (%), Mean
Baseline | 8.5 | 8.3
Change at Week 30 [Least squares means are based on a mixed model adjusting for treatment, pooled investigator, visit, baseline HbA1c value, and treatment by visit, where subject is treated as a random effect.] | -1.0 | -1.7
Difference from placebo (95% CI) |  | -0.7 [-1.0, -0.5] [p <0.01, treatment vs. placebo.]
Proportion Achieving HbA1c <7% | 30% | 57%
Body Weight (kg), Mean
Baseline | 93.8 | 95.4
Change at Week 30 [Least squares means are based on a mixed model adjusting for treatment, pooled investigator, visit, baseline HbA1c stratum, baseline value of the dependent variable (where applicable), and treatment by visit, where subject is treated as a random effect.] | 1.0 | -1.8
Difference from placebo (95% CI) |  | -2.7 [-3.7, -1.7]
Fasting Serum Glucose (mg/dL), Mean
Baseline | 133 | 132
Change at Week 30 | -16 | -23
Difference from placebo (95% CI) |  | -7 [-18, 3]
BID = twice daily.

Table 9: Dosing Algorithm for Titration of Insulin Glargine [Adapted from Riddle et al. 2003.]
Fasting Plasma Glucose Values (mg/dL) | Dose Change (U)
<56 [Value for at least 1 fasting plasma glucose measurement since the last assessment.] | -4
56 to 72 | -2
73 to 99 [Based on the average of fasting plasma glucose measurements taken over the prior 3 to 7 days. The increase in the total daily dose should not have exceeded more than 10 units per day or 10% of the current total daily dose, whichever was greater.] | 0
100 to 119 | +2
120 to 139 | +4
140 to 179 | +6
≥180 | +8
Abbreviations: U = units.

16 HOW SUPPLIED/STORAGE AND HANDLING

16.1 How Supplied

BYETTA is supplied as a sterile solution for subcutaneous injection containing 250 mcg/mL exenatide.

The following packages are available:
5 mcg per dose, 60 doses, 1.2 mL prefilled pen, NDC 54868-5384-0
10 mcg per dose, 60 doses, 2.4 mL prefilled pen, NDC 54868-5384-1

16.2 Storage and Handling

- Prior to first use, BYETTA must be stored refrigerated at 36ºF to 46ºF (2ºC to 8ºC).
- After first use, BYETTA can be kept at a temperature not to exceed 77ºF (25ºC).
- Do not freeze. Do not use BYETTA if it has been frozen.
- BYETTA should be protected from light.
- The pen should be discarded 30 days after first use, even if some drug remains in the pen.
- Use a puncture-resistant container to discard the needles. Do not reuse or share needles.
- BYETTA should not be used past the expiration date.
- BYETTA pens are not to be shared with other patients.

17 PATIENT COUNSELING INFORMATION

Patients should be advised that BYETTA pens are never to be shared with another patient.

Patients should be informed of the potential risks and benefits of BYETTA and of alternative modes of therapy. Patients should also be fully informed about self-management practices, including the importance of proper storage of BYETTA, injection technique, timing of dosage of BYETTA and concomitant oral drugs, adherence to meal planning, regular physical activity, periodic blood glucose monitoring and HbA1c testing, recognition and management of hypoglycemia and hyperglycemia, and assessment for diabetes complications.

17.1 Risk of Pancreatitis

Patients should be informed that persistent severe abdominal pain that may radiate to the back and which may or may not be accompanied by vomiting, is the hallmark symptom of acute pancreatitis. Patients should be instructed to promptly discontinue BYETTA and contact their physician if persistent severe abdominal pain occurs [see Warnings and Precautions (5.1)].

17.2 Risk of Hypoglycemia

The risk of hypoglycemia is increased when BYETTA is used in combination with a sulfonylurea. Therefore, patients receiving BYETTA and a sulfonylurea may require a lower dose of the sulfonylurea to reduce the risk of hypoglycemia. Patients should be informed that it is also possible that the use of BYETTA with other glucose-independent insulin secretagogues (e.g., meglitinides) could increase the risk of hypoglycemia.

When BYETTA is used in combination with insulin, evaluate the dose of insulin. Consider reducing the dose of insulin in patients at increased risk of hypoglycemia [see Adverse Reactions (6.1)]. Patients treated with BYETTA should be informed that the concurrent use of BYETTA with prandial insulin has not been studied and cannot be recommended.

The symptoms, treatment, and conditions that predispose to development of hypoglycemia should be explained to the patient. The patient's usual instructions for hypoglycemia management should be reviewed and reinforced when initiating BYETTA therapy, particularly when concomitantly administered with a sulfonylurea or insulin [see Warnings and Precautions (5.2)].

17.3 Risk of Renal Impairment

Patients treated with BYETTA should be informed of the potential risk for worsening renal function and informed about associated signs and symptoms of renal dysfunction, as well as the possibility of dialysis as a medical intervention if renal failure occurs [see Warnings and Precautions (5.3)].

17.4 Risk of Hypersensitivity Reactions

Patients should be informed that serious hypersensitivity reactions have been reported during postmarketing use of BYETTA. If symptoms of hypersensitivity reactions occur, patients must stop taking BYETTA and seek medical advice promptly [see Warnings and Precautions (5.6)].

17.5 Use in Pregnancy

Patients should be advised to inform their physicians if they are pregnant or intend to become pregnant.

17.6 Instructions

Each dose of BYETTA should be administered as a SC injection in the thigh, abdomen, or upper arm at any time within the 60-minute period before the morning and evening meals (or before the two main meals of the day, approximately 6 hours or more apart). BYETTA should not be administered after a meal. If a dose is missed, the treatment regimen should be resumed as prescribed with the next scheduled dose.

Patients should be advised that treatment with BYETTA may result in a reduction in appetite, food intake, and/or body weight, and that there is no need to modify the dosing regimen due to such effects. Treatment with BYETTA may also result in nausea, particularly upon initiation of therapy [see Adverse Reactions (6)].

The patient should read the Medication Guide and the Pen User Manual before starting BYETTA therapy and review them each time the prescription is refilled. The patient should be instructed on proper use and storage of the pen, emphasizing how and when to set up a new pen and noting that only one setup step is necessary at initial use. The patient should be advised not to share the pen and needles.

Patients should be informed that pen needles are not included with the pen and must be purchased separately. Patients should be advised which needle length and gauge should be used.

Manufactured for Amylin Pharmaceuticals, Inc., San Diego, CA 92121
1-800-868-1190

http://www.BYETTA.com

This product and its use are covered by US Patent Nos. 5,424,286, 6,858,576, 6,872,700, 6,902,744, 6,956,026, 7,297,761, 7,521,423, 7,741,269, and other patents pending.

Literature Revised December 2011

BYETTA is a registered trademark of Amylin Pharmaceuticals, Inc.

© 2005, 2011 Amylin Pharmaceuticals, Inc. All rights reserved.
822017-AA

Additional barcode labeling by:
Physicians Total Care, Inc.
Tulsa, Oklahoma 74146

Medication Guide

BYETTA® (bye-A-tuh)
(exenatide)
Injection

Read this Medication Guide and the Pen User Manual that come with BYETTA before you start using it and each time you get a refill. There may be new information. This Medication Guide does not take the place of talking with your healthcare provider about your medical condition or your treatment. If you have questions about BYETTA after reading this information, ask your healthcare provider or pharmacist.

What is the most important information I should know about BYETTA?

Serious side effects can happen in people who take BYETTA, including inflammation of the pancreas (pancreatitis) which may be severe and lead to death.

Before taking BYETTA, tell your healthcare provider if you have had:

- pancreatitis.
- stones in your gallbladder (gallstones).
- a history of alcoholism.
- high blood triglyceride levels.

These medical conditions can make you more likely to get pancreatitis in general. It is not known if having these conditions will lead to a higher chance of getting pancreatitis while taking BYETTA.

While taking BYETTA:

Call your healthcare provider right away if you have pain in your stomach area (abdomen) that is severe, and will not go away. The pain may happen with or without vomiting. The pain may be felt going from your abdomen through to your back. These may be symptoms of pancreatitis.

What is BYETTA?

- BYETTA is an injectable prescription medicine that may improve blood sugar (glucose) control in adults with type 2 diabetes mellitus, when used with a diet and exercise program.
- BYETTA is not insulin.
- You should not take BYETTA instead of insulin.
- The use of BYETTA with short acting insulin is not recommended.
- The use of BYETTA with rapid acting insulin is not recommended.
- BYETTA is not for people with type 1 diabetes or people with diabetic ketoacidosis.
- It is not known if BYETTA is safe and effective in children.
- BYETTA has not been studied in people who have pancreatitis.
- BYETTA should not be used in people who have severe kidney problems.

Who should not use BYETTA?

Do not use BYETTA if:

- you have had an allergic reaction to exenatide or any of the other ingredients in BYETTA. See the end of this Medication Guide for a complete list of ingredients in BYETTA.

Symptoms of a severe allergic reaction with BYETTA may include:

- swelling of your face, lips, tongue, or throat
- problems breathing or swallowing

- severe rash or itching
- fainting or feeling dizzy
- very rapid heartbeat

What should I tell my healthcare provider before using BYETTA?

Before taking BYETTA, tell your healthcare provider if you:

- have or have had pancreatitis, stones in your gallbladder (gallstones), a history of alcoholism, or high blood triglyceride levels.
- have severe problems with your stomach, such as delayed emptying of your stomach (gastroparesis) or problems with digesting food.
- have or have had kidney problems, or have had a kidney transplant.
- have any other medical conditions.
- are pregnant or plan to become pregnant. It is not known if BYETTA will harm your unborn baby.
  Pregnancy Registry: Amylin Pharmaceuticals, Inc. has a registry for women who take BYETTA during pregnancy. The purpose of this registry is to collect information about the health of you and your baby. If you take BYETTA at any time during pregnancy you may enroll in this registry by calling (800) 633-9081.
- are breastfeeding or plan to breast-feed. It is not known if BYETTA passes into your breast milk. You and your healthcare provider should decide if you will take BYETTA or breast-feed. You should not do both without talking with your healthcare provider first.

Tell your healthcare provider about all the medicines you take including prescription and nonprescription medicines, vitamins, and herbal supplements. BYETTA slows stomach emptying and can affect medicines that need to pass through the stomach quickly. BYETTA may affect the way some medicines work and some other medicines may affect the way BYETTA works.

Especially tell your healthcare provider if you take:

- Other anti-diabetes medicines, especially sulfonylurea medicines or insulin.
- birth control pills that are taken by mouth (oral contraceptives). BYETTA may lower the amount of the medicine in your blood from your birth control pills and they may not work as well to prevent pregnancy. Take your birth control pills at least one hour before your injection of BYETTA. If you must take your birth control pills with food, take it with a meal or snack where you do not also take BYETTA.
- an antibiotic. Take antibiotic medicines at least one hour before taking BYETTA. If you must take your antibiotic with food, take it with a meal or snack where you do not also take BYETTA.
- warfarin sodium (Coumadin®, Jantoven®).
- a blood pressure medicine.
- a water pill (diuretic).
- a pain medicine.
- lovastatin (Altoprev®, Mevacor®, Advicor®).

Ask your healthcare provider if you are not sure if your medicine is listed above.

Know the medicines you take. Keep a list of them with you to show your healthcare provider and pharmacist each time you get a new medicine.

How should I use BYETTA?

See the Pen User Manual that comes with BYETTA for instructions for using the BYETTA Pen and injecting BYETTA.

- Your healthcare provider may prescribe BYETTA alone or with certain other medicines to help control your blood sugar.
- BYETTA comes in a prefilled pen.
- Use BYETTA exactly as prescribed by your healthcare provider. Do not change your dose unless your healthcare provider has told you to change your dose.
- Your healthcare provider must teach you how to inject BYETTA before you use it for the first time. If you have questions or do not understand the instructions, talk to your healthcare provider or pharmacist.
- Pen needles are not included. You may need a prescription to purchase pen needles from your pharmacist. Ask your healthcare provider which needle length and gauge is best for you.
- Inject your dose of BYETTA under the skin (subcutaneous injection) of your upper leg (thigh), stomach area (abdomen), or upper arm as instructed by your healthcare provider. Do not inject into a vein or muscle.
- Do not mix BYETTA and insulin in the same syringe or vial even if you take them at the same time.
- BYETTA is injected two times each day, at any time within the 60 minutes (1 hour) before your morning and evening meals (or before the two main meals of the day, approximately 6 hours or more apart). Do not take BYETTA after your meal.
- If you miss a dose of BYETTA, skip that dose and take your next dose at the next prescribed time. Do not take an extra dose or increase the amount of your next dose to make up for a missed dose.
- If you use too much BYETTA, call your healthcare provider or poison control center right away. Too much BYETTA can cause your blood sugar to drop quickly and you may have symptoms of low blood sugar. You may need medical treatment right away. Too much BYETTA can also cause severe nausea and vomiting.
- Follow your healthcare provider's instructions for diet, exercise, and how often to test your blood sugar. If you see your blood sugar increasing during treatment with BYETTA, talk to your healthcare provider because you may need to adjust your current treatment plan for your diabetes.
- Talk to your healthcare provider about how to manage high blood sugar (hyperglycemia) and low blood sugar (hypoglycemia), and how to recognize problems that can happen with your diabetes.
- Never share your BYETTA pen with another person. You may give an infection to them, or get an infection from them, and BYETTA may harm them.

What are the possible side effects of BYETTA?

BYETTA can cause serious side effects.

See "What is the most important information I should know about BYETTA?"

It is not known whether BYETTA, or other anti-diabetes medications, increase your risk of a heart attack or stroke.

- Low blood sugar (hypoglycemia). Your risk for getting low blood sugar is higher if you take BYETTA with another medicine that can cause low blood sugar, such as a sulfonylurea or insulin. The dose of your sulfonylurea or insulin medicine may need to be lowered while you use BYETTA. Signs and symptoms of low blood sugar may include:
  - headache
  - drowsiness
  - weakness
  - dizziness
  - confusion
  - irritability
  - hunger
  - fast heart beat
  - sweating
  - feeling jittery

Talk with your healthcare provider about how to treat low blood sugar.

- Kidney problems. BYETTA may cause new or worse problems with kidney function, including kidney failure. Dialysis or kidney transplant may be needed.
  - While taking BYETTA:
    Call your healthcare provider right away if you have nausea, vomiting, or diarrhea that will not go away, or if you cannot take liquids by mouth. You may be at increased risk for kidney problems.
- Severe allergic reactions. Severe allergic reactions can happen with BYETTA. Stop taking BYETTA, and get medical help right away if you have any symptom of a severe allergic reaction. See "Who should not take BYETTA?"

The most common side effects with BYETTA include:

- nausea. Nausea most commonly happens when first starting BYETTA, but may become less over time.
- vomiting.
- diarrhea.
- feeling jittery.
- dizziness.
- headache.
- acid stomach.
- constipation.
- weakness.

Talk to your healthcare provider about any side effect that bothers you or that does not go away.

These are not all the side effects with BYETTA.

Call your doctor for medical advice about side effects. You may report side effects to FDA at 1-800-FDA-1088.

How should I store BYETTA?

- Store your new, unused BYETTA Pen in the original carton in a refrigerator at 36°F to 46°F (2°C to 8ºC).
- After first use, keep your BYETTA Pen at a temperature cooler than 77°F (25°C).
- Do not freeze your BYETTA Pen. Do not use BYETTA if it has been frozen.
- Protect BYETTA from light.
- Use a BYETTA Pen for only 30 days. Throw away a used BYETTA Pen after 30 days, even if there is some medicine left in the pen.
- Do not use BYETTA after the expiration date printed on the label.
- Do not store the BYETTA Pen with the needle attached. If the needle is left on, medicine may leak from the BYETTA Pen or air bubbles may form in the cartridge.
- See the BYETTA Pen User Manual for instructions about the right way to throw away your BYETTA Pen.
- Keep your BYETTA Pen, pen needles, and all medicines out of the reach of children.

General information about BYETTA

Medicines are sometimes prescribed for purposes other than those listed in a Medication Guide. Do not use BYETTA for a condition for which it was not prescribed. Do not give BYETTA to other people, even if they have the same symptoms you have. It may harm them.

This Medication Guide includes the most important information you should know about using BYETTA. If you would like more information, talk with your healthcare provider. You can ask your healthcare provider or pharmacist for information about BYETTA that is written for health professionals.

For more information about BYETTA, go to http://www.BYETTA.com or call BYETTA Customer Service at 1-800-868-1190.

What are the ingredients in BYETTA?

Active Ingredient: exenatide

Inactive Ingredients: metacresol, mannitol, glacial acetic acid, and sodium acetate trihydrate in water for injection.

This Medication Guide has been approved by the U.S. Food and Drug Administration.

Revised December 2011

Manufactured for Amylin Pharmaceuticals, Inc., San Diego, CA 92121

BYETTA is a registered trademark of Amylin Pharmaceuticals, Inc.
All other marks are the marks of their respective owners.

© 2005, 2011 Amylin Pharmaceuticals, Inc. All rights reserved. 823015-AA

INSTRUCTIONS FOR USE

5 mcg PEN USER MANUAL

Section 1
Read this section completely before you begin. Then, move on to Section 2–Getting Started.

WHAT YOU NEED TO KNOW ABOUT YOUR BYETTA PEN

Byetta®
exenatide injection
250 mcg/mL, 1.2 mL
5 mcg

PEN USER MANUAL

PEN USER MANUAL

Read these instructions carefully BEFORE using your BYETTA Pen. For complete dosing and safety information, also read the BYETTA Medication Guide that comes with the BYETTA Pen carton.

It is important that you use your pen correctly. Failure to follow these instructions completely may result in a wrong dose, a broken pen or an infection.

These instructions do not take the place of talking with your healthcare provider about your medical condition or your treatment. If you are having problems using your BYETTA Pen, call toll free 800-868-1190.

IMPORTANT INFORMATION ABOUT YOUR BYETTA PEN

- Each BYETTA Pen contains enough medicine for injection two times each day for 30 days. You do not have to measure any doses, the pen measures each dose for you.
- Do not transfer the medicine in the BYETTA Pen to a syringe or vial.
- Do not mix BYETTA and insulin in the same syringe or vial even if you take them at the same time.
- If any part of your pen appears broken or damaged, do not use the pen.
- This BYETTA Pen is not recommended for use by people who are blind or have vision problems without the help of a person trained in the proper use of the pen.
- Follow the injection method explained to you by your healthcare provider.
- Follow Section 2 only to set up a new pen before first use.
- Section 3 of this manual should be used for every injection.

ABOUT PEN NEEDLES

What kinds of needles can be used with my BYETTA Pen?

- Pen needles are not included with your pen. You may need a prescription to get them from your pharmacist.
- Use 29 (thin), 30, or 31 (thinner) gauge disposable pen needles with your BYETTA Pen. Ask your healthcare provider which needle gauge and length is best for you.

Do I use a new needle for each injection?

- Yes. Do not reuse needles.
- Remove the needle from the pen immediately after you complete each injection. This will help prevent leakage of BYETTA, keep out air bubbles, reduce needle clogs, and decrease the risk of infection.
- Do not push the injection button on your pen unless a needle is attached to the pen.

How do I throw away my needles?

- Do not throw away the pen with a needle attached.
- Place used needles in a closeable, puncture-resistant container. You may use a sharps container (such as a red biohazard container), a hard plastic container (such as a detergent bottle), or a metal container (such as an empty coffee can). Ask your healthcare provider for instructions on the right way to throw away (dispose of) your used pens and the container. There may be state and local laws about how you should throw away used pens and needles.
- Do not throw the disposal container in the household trash. Do not recycle.
- Always keep the puncture-proof container out of reach of children.

Never share your BYETTA pen or needles with another person. You may give an infection to them, or get an infection from them, and BYETTA may harm them.

STORING YOUR BYETTA PEN

How do I store my BYETTA Pen?

- Prior to first use, store your unused BYETTA Pen in the original carton in a refrigerator at 36°F to 46°F (2°C to 8°C).
- After first use, your BYETTA Pen can be kept at a temperature not to exceed 77°F (25°C).
- Do not freeze. Do not use BYETTA if it has been frozen. BYETTA should be protected from light.
- When carrying the pen away from home, store the pen at a temperature between 36°F to 77°F (2°C to 25°C) and keep dry.
- Do not store the pen with the needle attached. If the needle is left on the pen, BYETTA may leak from the pen and air bubbles may form in the cartridge.

Keep your pen and needles out of the reach of children.

How long can I use a BYETTA Pen?

- You can use your BYETTA Pen for up to 30 days after setting up a new pen for first use. After 30 days, throw away the BYETTA Pen, even if it is not completely empty.
- Mark the date when you first used your pen and the date 30 days later in the spaces below:

Date of First Use Date to Throw Away Pen

- BYETTA should not be used after the expiration date printed on the pen label.

How do I clean my BYETTA Pen?

- Wipe the outside of the pen with a clean, damp cloth.
- White particles may appear on the outside tip of the cartridge during normal use. You may remove them with an alcohol wipe or alcohol swab.

See the complete BYETTA Medication Guide
that comes with BYETTA. For more information,
call toll free 800-868-1190 or visit www.BYETTA.com

Section 2
Read and follow the directions in this section only after you've read Section 1—What You Need To Know About Your BYETTA Pen.

GETTING STARTED

Set up your new pen just before you use it the first time. For routine use, do not repeat this one-time-only new pen setup. If you do, you will run out of BYETTA before 30 days of use.

ONE-TIME-ONLY NEW PEN SETUP
STEP A Check the Pen
 |  | Note: A small air bubble in the cartridge is normal.
- Wash hands prior to use. - Check pen label to make sure it is your 5 mcg pen. - Pull off the blue pen cap. | - Check BYETTA in the cartridge. The liquid should be clear, colorless, and free of particles. If not, do not use.
STEP B Attach the Needle
- Remove paper tab from outer needle shield. - Push outer needle shield containing the needle straight onto the pen, then screw needle on until secure. | - Pull off outer needle shield. Do not throw away. | - Pull off inner needle shield and throw away. A small drop of liquid may appear. This is normal.
STEP C Dial the Dose
- Check that the is in the dose window. If not, turn dose knob away from you (clockwise) until it stops and the is in the dose window. | - Pull dose knob out until it stops and the is in the dose window. | - Turn dose knob away from you until it stops at . Make sure that the 5 with the line under it is in the center of the dose window.
Note: If you cannot turn the dose knob away from you to the , see Commonly Asked Questions, number 7, in Section 4 of this user manual.
STEP D Prepare the Pen
- Point the needle of the pen up and away from you. | PUSH & HOLD; - Use thumb to firmly push injection button in until it stops, then continue holding the injection button in while slowly counting to 5. - If you do not see a stream or several drops come from the needle tip, repeat Steps C & D. | - Pen preparation is complete when the is in the center of the dose window AND you have seen a stream or several drops come from the needle tip.
Note: If you do not see liquid after 4 times, see Commonly Asked Questions, number 3, in Section 4 of this user manual.
STEP E Complete New Pen Setup
- Turn dose knob away from you until it stops and the is in the dose window. | - For routine use, do not repeat this one-time-only new pen setup. If you do, you will run out of BYETTA before 30 days of use. | - You are now ready for your first dose of BYETTA. - Go to Section 3, Step 3, for instructions on how to inject your first routine dose.
Note: If you cannot turn the dose knob, see Commonly Asked Questions, number 7, in Section 4 of user manual.

Section 3
Now that you have done the one-time-only new pen setup, follow Section 3 for all of your injections.
ROUTINE USE
STEP 1 Check the Pen
- Wash hands prior to use. - Check pen label to make sure it is your 5 mcg pen. - Pull off the blue pen cap. | - Check BYETTA in the cartridge. - The liquid should be clear, colorless, and free of particles. If it is not, do not use. | Note: A small air bubble will not harm you or affect your dose.
STEP 2 Attach the Needle
- Remove paper tab from outer needle shield. - Push outer needle shield containing the needle straight onto pen, then screw needle on until secure. | - Pull off outer needle shield. Do not throw away. | - Pull off inner needle shield and throw away. A small drop of liquid may appear. This is normal.
STEP 3 Dial the Dose
- Check that the is in the dose window. If not, turn dose knob away from you (clockwise) until it stops and the is in the dose window. | - Pull dose knob out until it stops and the is in the dose window. | - Turn dose knob away from you until it stops at . Make sure that the 5 with the line under it is in the center of the dose window.
Note: If you cannot turn the dose knob away from you to the , see Commonly Asked Questions, number 7, in Section 4 of this user manual.
STEP 4 Inject the Dose
- Grip pen firmly. - Insert needle into skin using the under-the-skin (subcutaneous) injection method explained by your healthcare provider. | PUSH & HOLD; - Use thumb to firmly push injection button in until it stops. Continue holding in the injection button while slowly counting to 5 to get a full dose. - Remove needle from skin. | - Injection is complete when the is in the center of the dose window. - The pen is now ready to reset.
Note: If you see several drops of BYETTA leaking from the needle after the injection, you may not have received a complete dose. See Commonly Asked Questions, number 4, in Section 4 of this user manual.
STEP 5 Reset the Pen
 | - Turn dose knob away from you until it stops and the is in the dose window. | Note: If you cannot turn the dose knob, or if your pen leaks, your full dose has not been delivered. See Commonly Asked Questions, numbers 4 and 7, in Section 4 of this user manual.
STEP 6 Remove and Dispose of the Needle
- Carefully put the outer needle shield back over the needle. - Remove the needle after each injection. | - Unscrew the needle. | - Throw away needles in a puncture-resistant container or as recommended by your healthcare provider.
STEP 7 Store Pen for Next Dose

- Replace Blue Pen Cap on pen before storage.
- Store your BYETTA Pen at a temperature between 36°F to 77°F (2°C to 25°C). (See Storing Your BYETTA Pen in Section 1 of this user manual for complete storage information.)
- When it is time for your next routine dose, go to Section 3, Step 1, and repeat Steps 1–7.

Section 4

COMMONLY ASKED QUESTIONS

1. Do I need to do the One-Time-Only New Pen Setup before every dose?

- No. The One-Time-Only New Pen Setup is done only once, just before each new pen is used for the first time.
- The purpose of the setup is to make sure that your BYETTA Pen is ready to use for the next 30 days.
- If you repeat the One-Time-Only New Pen Setup before each routine dose, you will not have enough BYETTA for 30 days. The small amount of BYETTA used in the new pen setup will not affect the 30-day supply of BYETTA.

2. Why are there air bubbles in the cartridge?

- A small air bubble is normal. It will not harm you or affect your dose.
- If the pen is stored with a needle attached, air bubbles may form in the cartridge. Do not store the pen with the needle attached.

3. What should I do if BYETTA does not come out of the needle tip after four tries during One-Time-Only New Pen Setup?

- Carefully put the outer needle shield back over the needle. Remove the needle by unscrewing it. Throw away the needle properly.
- Attach a new needle and repeat One-Time-Only New Pen Setup, Steps B–E, in Section 2 of this user manual. Once you see several drops or a stream of liquid coming out of the tip of the needle, the setup is complete.

4. Why do I see BYETTA leaking from my needle after I have finished my injection?

It is normal for a single drop to remain on the tip of your needle after your injection is complete. If you see more than one drop:

- You may not have received your full dose. Do not inject another dose. Talk with your healthcare provider about what to do about a partial dose.
- To make sure that you get your full dose, when you take your injections, firmly push and hold the injection button in and slowly count to 5 (see Section 3, Step 4: Inject the Dose).

5. How can I tell when the injection is complete?

The injection is complete when:

- You have firmly pushed the injection button in all the way until it stops
  and
- You have slowly counted to 5 while you are still holding the injection button in and the needle is still in your skin
  and
- The is in the center of the dose window.

If you hear a click sound from your BYETTA Pen, ignore it. You must follow all the steps listed above to make sure your injection is complete.

6. Where should I inject BYETTA?

Inject BYETTA into your abdomen, thigh, or upper arm using the injection method explained to you by your healthcare provider.

7. What if I cannot pull, turn, or push the dose knob?

Check the symbol in the dose window. Follow the steps next to the matching symbol.
If is in the dose window:
  - Pull the dose knob out until appears.
If is in the dose window and the dose knob will not turn:
  - The cartridge in your BYETTA Pen may not have enough medicine to deliver a full dose. A small amount of BYETTA will always stay in the cartridge. If the cartridge contains a small amount and the dose knob will not turn, your pen does not have enough BYETTA and will not deliver any more doses. Obtain a new BYETTA Pen.
If and part of are in the dose window and the dose knob cannot be pushed in:
  - The dose knob was not turned all the way. Continue turning the dose knob away from you until is in the center of the dose window.
If part of and part of are in the dose window and the dose knob cannot be pushed in:
  - The needle may be clogged, bent, or incorrectly attached.
  - Attach a new needle. Make sure needle is on straight and screwed on all the way.
  - Firmly push the injection button in all the way. BYETTA should come from needle tip.
If is in the dose window and the dose knob will not turn:
  - The injection button was not pushed in all the way and a complete dose was not delivered. Talk with your healthcare provider about what to do about a partial dose.
  - Follow these steps to reset your pen for your next injection:
    - Firmly push the injection button in all the way until it stops. Keep holding the injection button in and slowly count to 5. Then release the injection button and turn the dose knob away from you until appears in the dose window.
    - If you cannot turn the dose knob, the needle may be clogged. Replace the needle and repeat the step above.
  - For your next dose, be sure to firmly push and hold the injection button in and slowly count to 5 before removing needle from skin.

See the complete BYETTA Medication Guide
that comes with BYETTA. For more information,
call toll free 800-868-1190 or visit www.BYETTA.com

Byetta®
exenatide injection

Manufactured for Amylin Pharmaceuticals, Inc., San Diego, CA 92121. All rights reserved. BYETTA is a registered trademark of Amylin Pharmaceuticals, Inc.
© 2007, 2011 Amylin Pharmaceuticals, Inc.
Literature revised December 2011
825001-08
PV 5017 UCP

INSTRUCTIONS FOR USE

10 mcg PEN USER MANUAL

Section 1
Read this section completely before you begin. Then, move on to Section 2—Getting Started.

WHAT YOU NEED TO KNOW ABOUT YOUR BYETTA PEN

Byetta®
exenatide injection
250 mcg/mL, 2.4 mL
10 mcg

PEN USER MANUAL

PEN USER MANUAL

Read these instructions carefully BEFORE using your BYETTA Pen. For complete dosing and safety information, also read the BYETTA Medication Guide that comes with the BYETTA Pen carton.

It is important that you use your pen correctly. Failure to follow these instructions completely may result in a wrong dose, a broken pen or an infection.

These instructions do not take the place of talking with your healthcare provider about your medical condition or your treatment. If you are having problems using your BYETTA Pen, call toll free 800-868-1190.

IMPORTANT INFORMATION ABOUT YOUR BYETTA PEN

- Each BYETTA Pen contains enough medicine for injection two times each day for 30 days. You do not have to measure any doses, the pen measures each dose for you.
- Do not transfer the medicine in the BYETTA Pen to a syringe or vial.
- Do not mix BYETTA and insulin in the same syringe or vial even if you take them at the same time.
- If any part of your pen appears broken or damaged, do not use the pen.
- This BYETTA Pen is not recommended for use by people who are blind or have vision problems without the help of a person trained in the proper use of the pen.
- Follow the injection method explained to you by your healthcare provider.
- Follow Section 2 only to set up a new pen before first use.
- Section 3 of this manual should be used for every injection.

ABOUT PEN NEEDLES

What kinds of needles can be used with my BYETTA Pen?

- Pen needles are not included with your pen. You may need a prescription to get them from your pharmacist.
- Use 29 (thin), 30, or 31 (thinner) gauge disposable pen needles with your BYETTA Pen. Ask your healthcare provider which needle gauge and length is best for you.

Do I use a new needle for each injection?

- Yes. Do not reuse needles.
- Remove the needle from the pen immediately after you complete each injection. This will help prevent leakage of BYETTA, keep out air bubbles, reduce needle clogs, and decrease the risk of infection.
- Do not push the injection button on your pen unless a needle is attached to the pen.

How do I throw away my needles?

- Do not throw away the pen with a needle attached.
- Place used needles in a closeable, puncture-resistant container. You may use a sharps container (such as a red biohazard container), a hard plastic container (such as a detergent bottle), or a metal container (such as an empty coffee can). Ask your healthcare provider for instructions on the right way to throw away (dispose of) your used pens and the container. There may be state and local laws about how you should throw away used pens and needles.
- Do not throw the disposal container in the household trash. Do not recycle.
- Always keep the puncture-proof container out of reach of children.

Never share your BYETTA pen or needles with another person. You may give an infection to them, or get an infection from them, and BYETTA may harm them.

STORING YOUR BYETTA PEN

How do I store my BYETTA Pen?

- Prior to first use, store your unused BYETTA Pen in the original carton in a refrigerator at 36°F to 46°F (2°C to 8°C).
- After first use, your BYETTA Pen can be kept at a temperature not to exceed 77°F (25°C).
- Do not freeze. Do not use BYETTA if it has been frozen. BYETTA should be protected from light.
- When carrying the pen away from home, store the pen at a temperature between 36°F to 77°F (2°C to 25°C) and keep dry.
- Do not store the pen with the needle attached. If the needle is left on the pen, BYETTA may leak from the pen and air bubbles may form in the cartridge.

Keep your pen and needles out of the reach of children.

How long can I use a BYETTA Pen?

- You can use your BYETTA Pen for up to 30 days after setting up a new pen for first use. After 30 days, throw away the BYETTA Pen, even if it is not completely empty.
- Mark the date when you first used your pen and the date 30 days later in the spaces below:

Date of First Use Date to Throw Away Pen

- BYETTA should not be used after the expiration date printed on the pen label.

How do I clean my BYETTA Pen?

- Wipe the outside of the pen with a clean, damp cloth.
- White particles may appear on the outside tip of the cartridge during normal use. You may remove them with an alcohol wipe or alcohol swab.

See the complete BYETTA Medication Guide
that comes with BYETTA. For more information,
call toll free 800-868-1190 or visit www.BYETTA.com

Section 2
Read and follow the directions in this section only after you've read Section 1—What You Need To Know About Your BYETTA Pen.

GETTING STARTED

Set up your new pen just before you use it the first time. For routine use, do not repeat this one-time-only new pen setup. If you do, you will run out of BYETTA before 30 days of use.

ONE-TIME-ONLY NEW PEN SETUP
STEP A Check the Pen
 |  | Note: A small air bubble in the cartridge is normal.
- Wash hands prior to use. - Check pen label to make sure it is your 10 mcg pen. - Pull off the blue pen cap. | - Check BYETTA in the cartridge. The liquid should be clear, colorless, and free of particles. If not, do not use.
STEP B Attach the Needle
- Remove paper tab from outer needle shield. - Push outer needle shield containing the needle straight onto the pen, then screw needle on until secure. | - Pull off outer needle shield. Do not throw away. | - Pull off inner needle shield and throw away. A small drop of liquid may appear. This is normal.
STEP C Dial the Dose
- Check that the is in the dose window. If not, turn dose knob away from you (clockwise) until it stops and the is in the dose window. | - Pull dose knob out until it stops and the is in the dose window. | - Turn dose knob away from you until it stops at . Make sure that the 10 with the line under it is in the center of the dose window.
Note: If you cannot turn the dose knob away from you to the , see Commonly Asked Questions, number 7, in Section 4 of this user manual.
STEP D Prepare the Pen
- Point the needle of the pen up and away from you. | PUSH & HOLD; - Use thumb to firmly push injection button in until it stops, then continue holding the injection button in while slowly counting to 5. - If you do not see a stream or several drops come from the needle tip, repeat Steps C & D. | - Pen preparation is complete when the is in the center of the dose window AND you have seen a stream or several drops come from the needle tip.
Note: If you do not see liquid after 4 times, see Commonly Asked Questions, number 3, in Section 4 of this user manual.
STEP E Complete New Pen Setup
- Turn dose knob away from you until it stops and the is in the dose window. | - For routine use, do not repeat this one-time-only new pen setup. If you do, you will run out of BYETTA before 30 days of use. | - You are now ready for your first dose of BYETTA. - Go to Section 3, Step 3, for instructions on how to inject your first routine dose.
Note: If you cannot turn the dose knob, see Commonly Asked Questions, number 7, in Section 4 of user manual.

Section 3
Now that you have done the one-time-only new pen setup, follow Section 3 for all of your injections.
ROUTINE USE
STEP 1 Check the Pen
- Wash hands prior to use. - Check pen label to make sure it is your 10 mcg pen. - Pull off the blue pen cap. | - Check BYETTA in the cartridge. - The liquid should be clear, colorless, and free of particles. If it is not, do not use. | Note: A small air bubble will not harm you or affect your dose.
STEP 2 Attach the Needle
- Remove paper tab from outer needle shield. - Push outer needle shield containing the needle straight onto pen, then screw needle on until secure. | - Pull off outer needle shield. Do not throw away. | - Pull off inner needle shield and throw away. A small drop of liquid may appear. This is normal.
STEP 3 Dial the Dose
- Check that the is in the dose window. If not, turn dose knob away from you (clockwise) until it stops and the is in the dose window. | - Pull dose knob out until it stops and the is in the dose window. | - Turn dose knob away from you until it stops at . Make sure that the 10 with the line under it is in the center of the dose window.
Note: If you cannot turn the dose knob away from you to the , see Commonly Asked Questions, number 7, in Section 4 of this user manual.
STEP 4 Inject the Dose
- Grip pen firmly. - Insert needle into skin using the under-the-skin (subcutaneous) injection method explained by your healthcare provider. | PUSH & HOLD; - Use thumb to firmly push injection button in until it stops. Continue holding in the injection button while slowly counting to 5 to get a full dose. - Remove needle from skin. | - Injection is complete when the is in the center of the dose window. - The pen is now ready to reset.
Note: If you see several drops of BYETTA leaking from the needle after the injection, you may not have received a complete dose. See Commonly Asked Questions, number 4, in Section 4 of this user manual.
STEP 5 Reset the Pen
 | - Turn dose knob away from you until it stops and the is in the dose window. | Note: If you cannot turn the dose knob, or if your pen leaks, your full dose has not been delivered. See Commonly Asked Questions, numbers 4 and 7, in Section 4 of this user manual.
STEP 6 Remove and Dispose of the Needle
- Carefully put the outer needle shield back over the needle. - Remove the needle after each injection. | - Unscrew the needle. | - Throw away needles in a puncture-resistant container or as recommended by your healthcare provider.
STEP 7 Store Pen for Next Dose

- Replace Blue Pen Cap on pen before storage.
- Store your BYETTA Pen at a temperature between 36°F to 77°F (2°C to 25°C). (See Storing Your BYETTA Pen in Section 1 of this user manual for complete storage information.)
- When it is time for your next routine dose, go to Section 3, Step 1, and repeat Steps 1–7.

Section 4

COMMONLY ASKED QUESTIONS

1. Do I need to do the One-Time-Only New Pen Setup before every dose?

- No. The One-Time-Only New Pen Setup is done only once, just before each new pen is used for the first time.
- The purpose of the setup is to make sure that your BYETTA Pen is ready to use for the next 30 days.
- If you repeat the One-Time-Only New Pen Setup before each routine dose, you will not have enough BYETTA for 30 days. The small amount of BYETTA used in the new pen setup will not affect the 30-day supply of BYETTA.

2. Why are there air bubbles in the cartridge?

- A small air bubble is normal. It will not harm you or affect your dose.
- If the pen is stored with a needle attached, air bubbles may form in the cartridge. Do not store the pen with the needle attached.

3. What should I do if BYETTA does not come out of the needle tip after four tries during One-Time-Only New Pen Setup?

- Carefully put the outer needle shield back over the needle. Remove the needle by unscrewing it. Throw away the needle properly.
- Attach a new needle and repeat One-Time-Only New Pen Setup, Steps B–E, in Section 2 of this user manual. Once you see several drops or a stream of liquid coming out of the tip of the needle, the setup is complete.

4. Why do I see BYETTA leaking from my needle after I have finished my injection?

It is normal for a single drop to remain on the tip of your needle after your injection is complete. If you see more than one drop:

- You may not have received your full dose. Do not inject another dose. Talk with your healthcare provider about what to do about a partial dose.
- To make sure that you get your full dose, when you take your injections, firmly push and hold the injection button in and slowly count to 5 (see Section 3, Step 4: Inject the Dose).

5. How can I tell when the injection is complete?

The injection is complete when:

- You have firmly pushed the injection button in all the way until it stops
  and
- You have slowly counted to 5 while you are still holding the injection button in and the needle is still in your skin
  and
- The is in the center of the dose window.

If you hear a click sound from your BYETTA Pen, ignore it. You must follow all the steps listed above to make sure your injection is complete.

6. Where should I inject BYETTA?

Inject BYETTA into your abdomen, thigh, or upper arm using the injection method explained to you by your healthcare provider.

7. What if I cannot pull, turn, or push the dose knob?

Check the symbol in the dose window. Follow the steps next to the matching symbol.
If is in the dose window:
  - Pull the dose knob out until appears.
If is in the dose window and the dose knob will not turn:
  - The cartridge in your BYETTA Pen may not have enough medicine to deliver a full dose. A small amount of BYETTA will always stay in the cartridge. If the cartridge contains a small amount and the dose knob will not turn, your pen does not have enough BYETTA and will not deliver any more doses. Obtain a new BYETTA Pen.
If and part of are in the dose window and the dose knob cannot be pushed in:
  - The dose knob was not turned all the way. Continue turning the dose knob away from you until is in the center of the dose window.
If part of and part of are in the dose window and the dose knob cannot be pushed in:
  - The needle may be clogged, bent, or incorrectly attached.
  - Attach a new needle. Make sure needle is on straight and screwed on all the way.
  - Firmly push the injection button in all the way. BYETTA should come from needle tip.
If is in the dose window and the dose knob will not turn:
  - The injection button was not pushed in all the way and a complete dose was not delivered. Talk with your healthcare provider about what to do about a partial dose.
  - Follow these steps to reset your pen for your next injection:
    - Firmly push the injection button in all the way until it stops. Keep holding the injection button in and slowly count to 5. Then release the injection button and turn the dose knob away from you until appears in the dose window.
    - If you cannot turn the dose knob, the needle may be clogged. Replace the needle and repeat the step above.
  - For your next dose, be sure to firmly push and hold the injection button in and slowly count to 5 before removing needle from skin.

See the complete BYETTA Medication Guide
that comes with BYETTA. For more information,
call toll free 800-868-1190 or visit www.BYETTA.com

Byetta®
exenatide injection

Manufactured for Amylin Pharmaceuticals, Inc., San Diego, CA 92121. All rights reserved. BYETTA is a registered trademark of Amylin Pharmaceuticals, Inc.
© 2007, 2011 Amylin Pharmaceuticals, Inc.
Literature revised December 2011
925001-08
PV 5027 UCP

PACKAGE LABEL

PRINCIPAL DISPLAY PANEL - 5 mcg

5
mcg

NDC 54868-5384-0

Byetta®
exenatide injection
250 mcg/mL, 1.2 mL

Dispense the enclosed Medication Guide to each patient

Each prefilled pen will deliver 60 subcutaneous doses, 5 mcg per dose
Rx Only

SUBCUTANEOUS USE ONLY REFRIGERATE – DO NOT FREEZE
DO NOT TRANSFER THIS MEDICATION TO A SYRINGE

Pen needles not included

Ask your healthcare provider which pen needle length and gauge is best for you
Use 29 (thin), 30, or 31 (thinner) gauge disposable pen needles